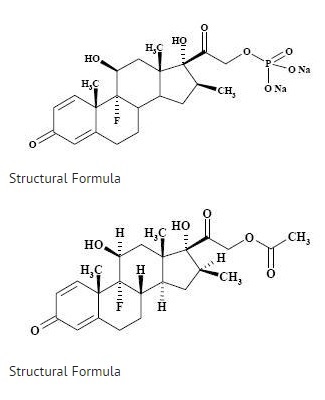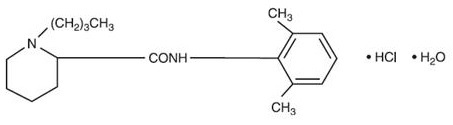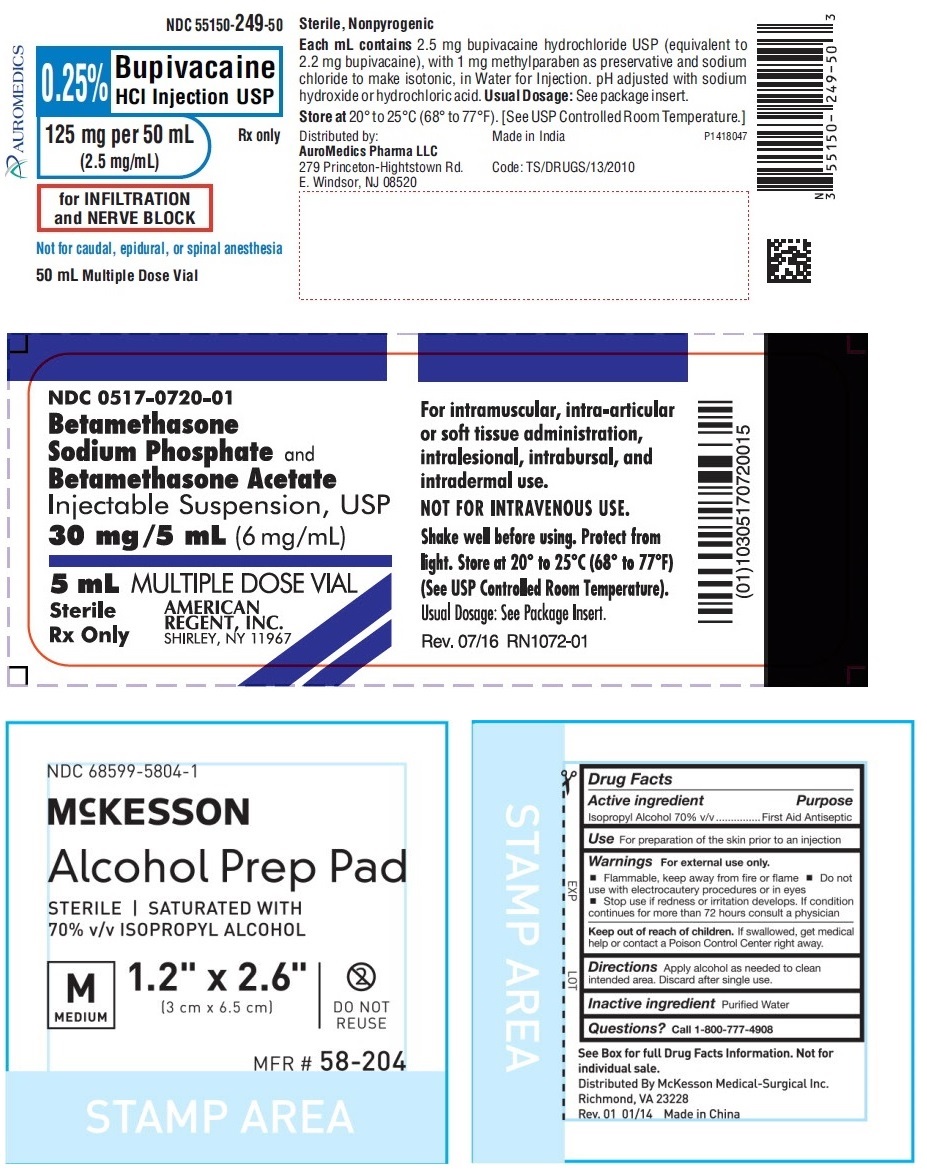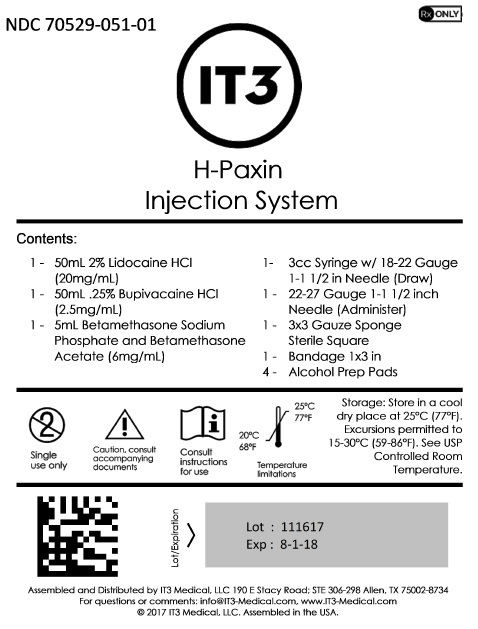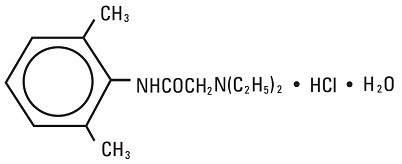 DRUG LABEL: H-Paxin
NDC: 70529-051 | Form: KIT | Route: INFILTRATION
Manufacturer: IT3 Medical LLC
Category: prescription | Type: HUMAN PRESCRIPTION DRUG LABEL
Date: 20220224

ACTIVE INGREDIENTS: LIDOCAINE HYDROCHLORIDE 20 mg/1 mL; BUPIVACAINE HYDROCHLORIDE 2.5 mg/1 mL; BETAMETHASONE ACETATE 3 mg/1 mL; BETAMETHASONE SODIUM PHOSPHATE 3 mg/1 mL; ISOPROPYL ALCOHOL 0.7 mL/1 mL
INACTIVE INGREDIENTS: SODIUM CHLORIDE 6 mg/1 mL; WATER; SODIUM HYDROXIDE; HYDROCHLORIC ACID; METHYLPARABEN 1 mg/1 mL; METHYLPARABEN; SODIUM CHLORIDE; SODIUM HYDROXIDE; HYDROCHLORIC ACID; WATER; SODIUM PHOSPHATE, DIBASIC, ANHYDROUS 7.1 mg/1 mL; SODIUM PHOSPHATE, MONOBASIC, MONOHYDRATE 3.4 mg/1 mL; EDETATE DISODIUM 0.1 mg/1 mL; BENZALKONIUM CHLORIDE 0.2 mg/1 mL; WATER; WATER

H-Paxin Injection System

Lidocaine Hydrochloride Injection, USP

AQUEOUS SOLUTIONS FOR
INFILTRATION AND NERVE BLOCK
Ampul
Plastic Multiple-dose Fliptop Vial
Glass Teartop Vial

Rx only

DESCRIPTION

Lidocaine Hydrochloride Injection, USP is a sterile, nonpyrogenic solution of lidocaine hydrochloride in water for injection for parenteral administration in various concentrations with characteristics as follows:

Concentration | 0.5% | 1% | 1.5% | 2%
mg/mL lidocaine HCl (anhyd.) | 5 | 10 | 15 | 20
mg/mL sodium chloride | 8 | 7 | 6.5 | 6

Multiple-dose vials contain 0.1% of methylparaben added as preservative. May contain sodium hydroxide and/or hydrochloric acid for pH adjustment. The pH is 6.5 (5.0 to 7.0). See HOW SUPPLIED section for various sizes and strengths.

Lidocaine is a local anesthetic of the amide type.

Lidocaine Hydrochloride, USP is chemically designated 2-(diethylamino)-N-(2,6-dimethylphenyl)-acetamide monohydrochloride monohydrate, a white powder freely soluble in water. The molecular weight is 288.82. It has the following structural formula:

The semi-rigid vial used for the plastic vials is fabricated from a specially formulated polyolefin. It is a copolymer of ethylene and propylene. The safety of the plastic has been confirmed by tests in animals according to USP biological standards for plastic containers. The container requires no vapor barrier to maintain the proper drug concentration.

CLINICAL PHARMACOLOGY

Mechanism of Action

Lidocaine HCl stabilizes the neuronal membrane by inhibiting the ionic fluxes required for the initiation and conduction of impulses thereby effecting local anesthetic action.

Hemodynamics

Excessive blood levels may cause changes in cardiac output, total peripheral resistance, and mean arterial pressure. With central neural blockade these changes may be attributable to block of autonomic fibers, a direct depressant effect of the local anesthetic agent on various components of the cardiovascular system, and/or the beta-adrenergic receptor stimulating action of epinephrine when present. The net effect is normally a modest hypotension when the recommended dosages are not exceeded.

Pharmacokinetics and Metabolism

Information derived from diverse formulations, concentrations and usages reveals that lidocaine HCl is completely absorbed following parenteral administration, its rate of absorption depending, for example, upon various factors such as the site of administration and the presence or absence of a vasoconstrictor agent. Except for intravascular administration, the highest blood levels are obtained following intercostal nerve block and the lowest after subcutaneous administration.

The plasma binding of lidocaine HCl is dependent on drug concentration, and the fraction bound decreases with increasing concentration. At concentrations of 1 to 4 mcg of free base per mL 60 to 80 percent of lidocaine HCl is protein bound. Binding is also dependent on the plasma concentration of the alpha-1-acid glycoprotein.

Lidocaine HCl crosses the blood-brain and placental barriers, presumably by passive diffusion.

Lidocaine HCl is metabolized rapidly by the liver, and metabolites and unchanged drug are excreted by the kidneys. Biotransformation includes oxidative N-dealkylation, ring hydroxylation, cleavage of the amide linkage, and conjugation. N-dealkylation, a major pathway of biotransformation, yields the metabolites monoethylglycinexylidide and glycinexylidide. The pharmacological/toxicological actions of these metabolites are similar to, but less potent than, those of lidocaine HCl. Approximately 90% of lidocaine HCl administered is excreted in the form of various metabolites, and less than 10% is excreted unchanged. The primary metabolite in urine is a conjugate of 4-hydroxy-2,6-dimethylaniline.

The elimination half-life of lidocaine HCl following an intravenous bolus injection is typically 1.5 to 2 hours. Because of the rapid rate at which lidocaine HCl is metabolized, any condition that affects liver function may alter lidocaine HCl kinetics. The half-life may be prolonged two-fold or more in patients with liver dysfunction. Renal dysfunction does not affect lidocaine HCl kinetics but may increase the accumulation of metabolites.

Factors such as acidosis and the use of CNS stimulants and depressants affect the CNS levels of lidocaine HCl required to produce overt systemic effects. Objective adverse manifestations become increasingly apparent with increasing venous plasma levels above 6 mcg free base per mL. In the rhesus monkey arterial blood levels of 18 to 21 mcg/mL have been shown to be threshold for convulsive activity.

INDICATIONS AND USAGE

Lidocaine Hydrochloride Injection, USP is indicated for production of local or regional anesthesia by infiltration techniques such as percutaneous injection and intravenous regional anesthesia by peripheral nerve block techniques such as brachial plexus and intercostal and by central neural techniques such as lumbar and caudal epidural blocks, when the accepted procedures for these techniques as described in standard textbooks are observed.

CONTRAINDICATIONS

Lidocaine HCl is contraindicated in patients with a known history of hypersensitivity to local anesthetics of the amide type.

WARNINGS

LIDOCAINE HYDROCHLORIDE INJECTION, FOR INFILTRATION AND NERVE BLOCK, SHOULD BE EMPLOYED ONLY BY CLINICIANS WHO ARE WELL VERSED IN DIAGNOSIS AND MANAGEMENT OF DOSE-RELATED TOXICITY AND OTHER ACUTE EMERGENCIES THAT MIGHT ARISE FROM THE BLOCK TO BE EMPLOYED AND THEN ONLY AFTER ENSURING THE IMMEDIATE AVAILABILITY OF OXYGEN, OTHER RESUSCITATIVE DRUGS, CARDIOPULMONARY EQUIPMENT AND THE PERSONNEL NEEDED FOR PROPER MANAGEMENT OF TOXIC REACTIONS AND RELATED EMERGENCIES (see also ADVERSE REACTIONS and PRECAUTIONS). DELAY IN PROPER MANAGEMENT OF DOSE-RELATED TOXICITY, UNDERVENTILATION FROM ANY CAUSE AND/OR ALTERED SENSITIVITY MAY LEAD TO THE DEVELOPMENT OF ACIDOSIS, CARDIAC ARREST AND, POSSIBLY, DEATH.

Intra-articular infusions of local anesthetics following arthroscopic and other surgical procedures is an unapproved use, and there have been post-marketing reports of chondrolysis in patients receiving such infusions. The majority of reported cases of chondrolysis have involved the shoulder joint; cases of gleno-humeral chondrolysis have been described in pediatric and adult patients following intra-articular infusions of local anesthetics with and without epinephrine for periods of 48 to 72 hours. There is insufficient information to determine whether shorter infusion periods are not associated with these findings. The time of onset of symptoms, such as joint pain, stiffness and loss of motion can be variable, but may begin as early as the 2nd month after surgery. Currently, there is no effective treatment for chondrolysis; patients who experienced chondrolysis have required additional diagnostic and therapeutic procedures and some required arthroplasty or shoulder replacement.

To avoid intravascular injection, aspiration should be performed before the local anesthetic solution is injected. The needle must be repositioned until no return of blood can be elicited by aspiration. Note, however, that the absence of blood in the syringe does not guarantee that intravascular injection has been avoided.

Local anesthetic solutions containing antimicrobial preservatives (e.g., methylparaben) should not be used for epidural or spinal anesthesia because the safety of these agents has not been established with regard to intrathecal injection, either intentional or accidental.

Anaphylactic reactions may occur following administration of lidocaine hydrochloride (see ADVERSE REACTIONS).

In the case of severe reaction, discontinue the use of the drug.

PRECAUTIONS

General

The safety and effectiveness of lidocaine HCl depend on proper dosage, correct technique, adequate precautions, and readiness for emergencies. Standard textbooks should be consulted for specific techniques and precautions for various regional anesthetic procedures.

Resuscitative equipment, oxygen, and other resuscitative drugs should be available for immediate use (see WARNINGS and ADVERSE REACTIONS). The lowest dosage that results in effective anesthesia should be used to avoid high plasma levels and serious adverse effects. Syringe aspirations should also be performed before and during each supplemental injection when using indwelling catheter techniques. During the administration of epidural anesthesia, it is recommended that a test dose be administered initially and that the patient be monitored for central nervous system toxicity and cardiovascular toxicity, as well as for signs of unintended intrathecal administration, before proceeding. When clinical conditions permit, consideration should be given to employing local anesthetic solutions that contain epinephrine for the test dose because circulatory changes compatible with epinephrine may also serve as a warning sign of unintended intravascular injection. An intravascular injection is still possible even if aspirations for blood are negative. Repeated doses of lidocaine HCl may cause significant increases in blood levels with each repeated dose because of slow accumulation of the drug or its metabolites. Tolerance to elevated blood levels varies with the status of the patient. Debilitated, elderly patients, acutely ill patients, and children should be given reduced doses commensurate with their age and physical condition. Lidocaine HCl should also be used with caution in patients with severe shock or heart block. Lumbar and caudal epidural anesthesia should be used with extreme caution in persons with the following conditions: existing neurological disease, spinal deformities, septicemia, and severe hypertension.

Local anesthetic solutions containing a vasoconstrictor should be used cautiously and in carefully circumscribed quantities in areas of the body supplied by end arteries or having otherwise compromised blood supply. Patients with peripheral vascular disease and those with hypertensive vascular disease may exhibit exaggerated vasoconstrictor response. Ischemic injury or necrosis may result. Preparations containing a vasoconstrictor should be used with caution in patients during or following the administration of potent general anesthetic agents, since cardiac arrhythmias may occur under such conditions.

Careful and constant monitoring of cardiovascular and respiratory (adequacy of ventilation) vital signs and the patient's state of consciousness should be accomplished after each local anesthetic injection. It should be kept in mind at such times that restlessness, anxiety, tinnitus, dizziness, blurred vision, tremors, depression or drowsiness may be early warning signs of central nervous system toxicity.

Since amide-type local anesthetics are metabolized by the liver, lidocaine should be used with caution in patients with hepatic disease. Patients with severe hepatic disease, because of their inability to metabolize local anesthetics normally, are at greater risk of developing toxic plasma concentrations. Lidocaine should also be used with caution in patients with impaired cardiovascular function since they may be less able to compensate for functional changes associated with the prolongation of A-V conduction produced by these drugs. Many drugs used during the conduct of anesthesia are considered potential triggering agents for familial malignant hyperthermia. Since it is not known whether amide-type local anesthetics may trigger this reaction and since the need for supplemental general anesthesia cannot be predicted in advance, it is suggested that a standard protocol for the management of malignant hyperthermia should be available. Early unexplained signs of tachycardia, tachypnea, labile blood pressure and metabolic acidosis may precede temperature elevation. Successful outcome is dependent on early diagnosis, prompt discontinuance of the suspect triggering agent(s) and institution of treatment, including oxygen therapy, indicated supportive measures and dantrolene (consult dantrolene sodium intravenous package insert before using).

Proper tourniquet technique, as described in publications and standard textbooks, is essential in the performance of intravenous regional anesthesia. Solutions containing epinephrine or other vasoconstrictors should not be used for this technique.

Lidocaine HCl should be used with caution in persons with known drug sensitivities. Patients allergic to para-aminobenzoic acid derivatives (procaine, tetracaine, benzocaine, etc.) have not shown cross-sensitivity to lidocaine HCl.

Use in the Head and Neck Area

Small doses of local anesthetics injected into the head and neck area, including retrobulbar, dental and stellate ganglion blocks, may produce adverse reactions similar to systemic toxicity seen with unintentional intravascular injections of larger doses. Confusion, convulsions, respiratory depression and/or respiratory arrest, and cardiovascular stimulation or depression have been reported. These reactions may be due to intra-arterial injections of the local anesthetic with retrograde flow to the cerebral circulation. Patients receiving these blocks should have their circulation and respiration monitored and be constantly observed. Resuscitative equipment and personnel for treating adverse reactions should be immediately available. Dosage recommendations should not be exceeded (see DOSAGE AND ADMINISTRATION).

Information for Patients

When appropriate, patients should be informed in advance that they may experience temporary loss of sensation and motor activity, usually in the lower half of the body, following proper administration of epidural anesthesia.

Clinically Significant Drug Interactions

The administration of local anesthetic solutions containing epinephrine or norepinephrine to patients receiving monoamine oxidase inhibitors or tricyclic anti-depressants may produce severe, prolonged hypertension.

Phenothiazines and butyrophenones may reduce or reverse the pressor effect of epinephrine.

Concurrent use of these agents should generally be avoided. In situations when concurrent therapy is necessary, careful patient monitoring is essential.

Concurrent administration of vasopressor drugs (for the treatment of hypotension related to obstetric blocks) and ergot-type oxytocic drugs may cause severe, persistent hypertension or cerebrovascular accidents.

Drug/Laboratory Test Interactions

The intramuscular injection of lidocaine HCl may result in an increase in creatine phosphokinase levels. Thus, the use of this enzyme determination, without isoenzyme separation, as a diagnostic test for the presence of acute myocardial infarction may be compromised by the intramuscular injection of lidocaine HCl.

Carcinogenesis, Mutagenesis, Impairment of Fertility

Studies of lidocaine HCl in animals to evaluate the carcinogenic and mutagenic potential or the effect on fertility have not been conducted.

Pregnancy

Teratogenic Effects

Reproduction studies have been performed in rats at doses up to 6.6 times the human dose and have revealed no evidence of harm to the fetus caused by lidocaine HCl. There are, however, no adequate and well-controlled studies in pregnant women. Animal reproduction studies are not always predictive of human response. General consideration should be given to this fact before administering lidocaine HCl to women of childbearing potential, especially during early pregnancy when maximum organogenesis takes place.

Labor and Delivery

Local anesthetics rapidly cross the placenta and when used for epidural, paracervical, pudendal or caudal block anesthesia, can cause varying degrees of maternal, fetal and neonatal toxicity (see CLINICAL PHARMACOLOGY, Pharmacokinetics and Metabolism). The potential for toxicity depends upon the procedure performed, the type and amount of drug used, and the technique of drug administration. Adverse reactions in the parturient, fetus and neonate involve alterations of the central nervous system, peripheral vascular tone and cardiac function.

Maternal hypotension has resulted from regional anesthesia. Local anesthetics produce vasodilation by blocking sympathetic nerves. Elevating the patient's legs and positioning her on her left side will help prevent decreases in blood pressure. The fetal heart rate also should be monitored continuously, and electronic fetal monitoring is highly advisable.

Epidural, spinal, paracervical, or pudendal anesthesia may alter the forces of parturition through changes in uterine contractility or maternal expulsive efforts. In one study, paracervical block anesthesia was associated with a decrease in the mean duration of first stage labor and facilitation of cervical dilation. However, spinal and epidural anesthesia have also been reported to prolong the second stage of labor by removing the parturient's reflex urge to bear down or by interfering with motor function. The use of obstetrical anesthesia may increase the need for forceps assistance.

The use of some local anesthetic drug products during labor and delivery may be followed by diminished muscle strength and tone for the first day or two of life. The long-term significance of these observations is unknown. Fetal bradycardia may occur in 20 to 30 percent of patients receiving paracervical nerve block anesthesia with the amide-type local anesthetics and may be associated with fetal acidosis. Fetal heart rate should always be monitored during paracervical anesthesia. The physician should weigh the possible advantages against risks when considering a paracervical block in prematurity, toxemia of pregnancy, and fetal distress. Careful adherence to recommended dosage is of the utmost importance in obstetrical paracervical block. Failure to achieve adequate analgesia with recommended doses should arouse suspicion of intravascular or fetal intracranial injection. Cases compatible with unintended fetal intracranial injection of local anesthetic solution have been reported following intended paracervical or pudendal block or both. Babies so affected present with unexplained neonatal depression at birth, which correlates with high local anesthetic serum levels, and often manifest seizures within six hours. Prompt use of supportive measures combined with forced urinary excretion of the local anesthetic has been used successfully to manage this complication.

Case reports of maternal convulsions and cardiovascular collapse following use of some local anesthetics for paracervical block in early pregnancy (as anesthesia for elective abortion) suggest that systemic absorption under these circumstances may be rapid. The recommended maximum dose of each drug should not be exceeded. Injection should be made slowly and with frequent aspiration. Allow a 5-minute interval between sides.

Nursing Mothers

It is not known whether this drug is excreted in human milk. Because many drugs are excreted in human milk, caution should be exercised when lidocaine HCl is administered to a nursing woman.

Pediatric Use

Dosages in children should be reduced, commensurate with age, body weight and physical condition (see DOSAGE AND ADMINISTRATION).

ADVERSE REACTIONS

Systemic

Adverse experiences following the administration of lidocaine HCl are similar in nature to those observed with other amide local anesthetic agents. These adverse experiences are, in general, dose-related and may result from high plasma levels caused by excessive dosage, rapid absorption or inadvertent intravascular injection, or may result from a hypersensitivity, idiosyncrasy or diminished tolerance on the part of the patient. Serious adverse experiences are generally systemic in nature. The following types are those most commonly reported:

Central Nervous System

CNS manifestations are excitatory and/or depressant and may be characterized by lightheadedness, nervousness, apprehension, euphoria, confusion, dizziness, drowsiness, tinnitus, blurred or double vision, vomiting, sensations of heat, cold or numbness, twitching, tremors, convulsions, unconsciousness, respiratory depression and arrest. The excitatory manifestations may be very brief or may not occur at all, in which case the first manifestation of toxicity may be drowsiness merging into unconsciousness and respiratory arrest.

Drowsiness following the administration of lidocaine HCl is usually an early sign of a high blood level of the drug and may occur as a consequence of rapid absorption.

Cardiovascular System

Cardiovascular manifestations are usually depressant and are characterized by bradycardia, hypotension, and cardiovascular collapse, which may lead to cardiac arrest.

Allergic

Allergic reactions are characterized by cutaneous lesions, urticaria, edema or anaphylactoid reactions. Allergic reactions may occur as a result of sensitivity either to local anesthetic agents or to the methylparaben used as a preservative in the multiple dose vials. Allergic reactions, including anaphylactic reactions, may occur as a result of sensitivity to lidocaine, but are infrequent. If allergic reactions do occur, they should be managed by conventional means. The detection of sensitivity by skin testing is of doubtful value.

There have been no reports of cross sensitivity between lidocaine hydrochloride and procainamide or between lidocaine hydrochloride and quinidine.

Neurologic

The incidences of adverse reactions associated with the use of local anesthetics may be related to the total dose of local anesthetic administered and are also dependent upon the particular drug used, the route of administration and the physical status of the patient. In a prospective review of 10,440 patients who received lidocaine HCl for spinal anesthesia, the incidences of adverse reactions were reported to be about 3 percent each for positional headaches, hypotension and backache; 2 percent for shivering; and less than 1 percent each for peripheral nerve symptoms, nausea, respiratory inadequacy and double vision. Many of these observations may be related to local anesthetic techniques, with or without a contribution from the local anesthetic.

In the practice of caudal or lumbar epidural block, occasional unintentional penetration of the subarachnoid space by the catheter may occur. Subsequent adverse effects may depend partially on the amount of drug administered subdurally. These may include spinal block of varying magnitude (including total spinal block), hypotension secondary to spinal block, loss of bladder and bowel control, and loss of perineal sensation and sexual function. Persistent motor, sensory and/or autonomic (sphincter control) deficit of some lower spinal segments with slow recovery (several months) or incomplete recovery have been reported in rare instances when caudal or lumbar epidural block has been attempted. Backache and headache have also been noted following use of these anesthetic procedures.

There have been reported cases of permanent injury to extraocular muscles requiring surgical repair following retrobulbar administration.

Hematologic

Methemoglobinemia.

OVERDOSAGE

Acute emergencies from local anesthetics are generally related to high plasma levels encountered during therapeutic use of local anesthetics or to unintended subarachnoid injection of local anesthetic solution (see ADVERSE REACTIONS, WARNINGS, and PRECAUTIONS).

Management of Local Anesthetic Emergencies

The first consideration is prevention, best accomplished by careful and constant monitoring of cardiovascular and respiratory vital signs and the patient's state of consciousness after each local anesthetic injection. At the first sign of change, oxygen should be administered.

The first step in the management of convulsions, as well as underventilation or apnea due to unintended subarachnoid injection of drug solution, consists of immediate attention to the maintenance of a patent airway and assisted or controlled ventilation with oxygen and a delivery system capable of permitting immediate positive airway pressure by mask. Immediately after the institution of these ventilatory measures, the adequacy of the circulation should be evaluated, keeping in mind that drugs used to treat convulsions sometimes depress the circulation when administered intravenously. Should convulsions persist despite adequate respiratory support, and if the status of the circulation permits, small increments of an ultra-short acting barbiturate (such as thiopental or thiamylal) or a benzodiazepine (such as diazepam) may be administered intravenously. The clinician should be familiar, prior to the use of local anesthetics, with these anticonvulsant drugs. Supportive treatment of circulatory depression may require administration of intravenous fluids and, when appropriate, a vasopressor as directed by the clinical situation (e.g., ephedrine).

If not treated immediately, both convulsions and cardiovascular depression can result in hypoxia, acidosis, bradycardia, arrhythmias and cardiac arrest. Underventilation or apnea due to unintentional subarachnoid injection of local anesthetic solution may produce these same signs and also lead to cardiac arrest if ventilatory support is not instituted. If cardiac arrest should occur, standard cardiopulmonary resuscitative measures should be instituted.

Endotracheal intubation, employing drugs and techniques familiar to the clinician, may be indicated, after initial administration of oxygen by mask, if difficulty is encountered in the maintenance of a patent airway or if prolonged ventilatory support (assisted or controlled) is indicated.

Dialysis is of negligible value in the treatment of acute overdosage with lidocaine HCl.

The oral LD50 of lidocaine HCl in non-fasted female rats is 459 (346 to 773) mg/kg (as the salt) and 214 (159 to 324) mg/kg (as the salt) in fasted female rats.

DOSAGE AND ADMINISTRATION

Table 1 (Recommended Dosages) summarizes the recommended volumes and concentrations of Lidocaine Hydrochloride Injection, USP for various types of anesthetic procedures. The dosages suggested in this table are for normal healthy adults and refer to the use of epinephrine-free solutions. When larger volumes are required, only solutions containing epinephrine should be used except in those cases where vasopressor drugs may be contraindicated.

There have been adverse event reports of chondrolysis in patients receiving intra-articular infusions of local anesthetics following arthroscopic and other surgical procedures. Lidocaine is not approved for this use (see WARNINGS and DOSAGE AND ADMINISTRATION).

These recommended doses serve only as a guide to the amount of anesthetic required for most routine procedures. The actual volumes and concentrations to be used depend on a number of factors such as type and extent of surgical procedure, depth of anesthesia and degree of muscular relaxation required, duration of anesthesia required, and the physical condition of the patient. In all cases the lowest concentration and smallest dose that will produce the desired result should be given. Dosages should be reduced for children and for the elderly and debilitated patients and patients with cardiac and/or liver disease.

The onset of anesthesia, the duration of anesthesia and the degree of muscular relaxation are proportional to the volume and concentration (i.e., total dose) of local anesthetic used. Thus, an increase in volume and concentration of Lidocaine Hydrochloride Injection will decrease the onset of anesthesia, prolong the duration of anesthesia, provide a greater degree of muscular relaxation and increase the segmental spread of anesthesia. However, increasing the volume and concentration of Lidocaine Hydrochloride Injection may result in a more profound fall in blood pressure when used in epidural anesthesia. Although the incidence of side effects with lidocaine HCl is quite low, caution should be exercised when employing large volumes and concentrations, since the incidence of side effects is directly proportional to the total dose of local anesthetic agent injected.

For intravenous regional anesthesia, only the 50 mL single-dose vial containing 0.5% Lidocaine Hydrochloride Injection, USP should be used.

Epidural Anesthesia

For epidural anesthesia, only the following available specific products of Lidocaine Hydrochloride Injection by Hospira are recommended:

1% | 30 mL single-dose teartop vials
1.5% | 20 mL single-dose ampuls
2% | 10 mL single-dose ampuls

Although these solutions are intended specifically for epidural anesthesia, they may also be used for infiltration and peripheral nerve block, provided they are employed as single dose units. These solutions contain no bacteriostatic agent. In epidural anesthesia, the dosage varies with the number of dermatomes to be anesthetized (generally 2 to 3 mL of the indicated concentration per dermatome).

Caudal and Lumbar Epidural Block

As a precaution against the adverse experience sometimes observed following unintentional penetration of the subarachnoid space, a test dose such as 2 to 3 mL of 1.5% lidocaine HCl should be administered at least 5 minutes prior to injecting the total volume required for a lumbar or caudal epidural block. The test dose should be repeated if the patient is moved in a manner that may have displaced the catheter. Epinephrine, if contained in the test dose (10 to 15 mcg have been suggested), may serve as a warning of unintentional intravascular injection. If injected into a blood vessel, this amount of epinephrine is likely to produce a transient "epinephrine response" within 45 seconds, consisting of an increase in heart rate and systolic blood pressure, circumoral pallor, palpitations and nervousness in the unsedated patient. The sedated patient may exhibit only a pulse rate increase of 20 or more beats per minute for 15 or more seconds. Patients on beta-blockers may not manifest changes in heart rate, but blood pressure monitoring can detect an evanescent rise in systolic blood pressure. Adequate time should be allowed for onset of anesthesia after administration of each test dose. The rapid injection of a large volume of Lidocaine Hydrochloride Injection through the catheter should be avoided, and, when feasible, fractional doses should be administered.

In the event of the known injection of a large volume of local anesthetic solution into the subarachnoid space, after suitable resuscitation and if the catheter is in place, consider attempting the recovery of drug by draining a moderate amount of cerebrospinal fluid (such as 10 mL) through the epidural catheter.

Maximum Recommended Dosages

NOTE: The products accompanying this insert do not contain epinephrine.

Adults

For normal healthy adults, the individual maximum recommended dose of lidocaine HCl with epinephrine should not exceed 7 mg/kg (3.5 mg/lb) of body weight, and in general it is recommended that the maximum total dose not exceed 500 mg. When used without epinephrine the maximum individual dose should not exceed 4.5 mg/kg (2 mg/lb) of body weight, and in general it is recommended that the maximum total dose does not exceed 300 mg. For continuous epidural or caudal anesthesia, the maximum recommended dosage should not be administered at intervals of less than 90 minutes. When continuous lumbar or caudal epidural anesthesia is used for non-obstetrical procedures, more drug may be administered if required to produce adequate anesthesia.

The maximum recommended dose per 90 minute period of lidocaine hydrochloride for paracervical block in obstetrical patients and non-obstetrical patients is 200 mg total. One-half of the total dose is usually administered to each side. Inject slowly, five minutes between sides (see also discussion of paracervical block in PRECAUTIONS).

For intravenous regional anesthesia, the dose administered should not exceed 4 mg/kg in adults.

Children

It is difficult to recommend a maximum dose of any drug for children, since this varies as a function of age and weight. For children over 3 years of age who have a normal lean body mass and normal body development, the maximum dose is determined by the child's age and weight. For example, in a child of 5 years weighing 50 lbs the dose of lidocaine HCl should not exceed 75 to 100 mg (1.5 to 2 mg/lb). The use of even more dilute solutions (i.e., 0.25 to 0.5%) and total dosages not to exceed 3 mg/kg (1.4 mg/lb) are recommended for induction of intravenous regional anesthesia in children.

In order to guard against systemic toxicity, the lowest effective concentration and lowest effective dose should be used at all times. In some cases it will be necessary to dilute available concentrations with 0.9% sodium chloride injection in order to obtain the required final concentration.

NOTE: Parenteral drug products should be inspected visually for particulate matter and discoloration prior to administration whenever the solution and container permit. Solutions that are discolored and/or contain particulate matter should not be used.

Table 1 Recommended Dosages
 | Lidocaine Hydrochloride Injection, USP (without Epinephrine)
Procedure | Conc. (%) | Vol. (mL) | Total Dose (mg)
Infiltration
Percutaneous | 0.5 or 1 | 1 to 60 | 5 to 300
Intravenous regional | 0.5 | 10 to 60 | 50 to 300
Peripheral Nerve Blocks, e.g.
Brachial | 1.5 | 15 to 20 | 225 to 300
Dental | 2 | 1 to 5 | 20 to 100
Intercostal | 1 | 3 | 30
Paravertebral | 1 | 3 to 5 | 30 to 50
Pudendal (each side) | 1 | 10 | 100
Paracervical
Obstetrical analgesia (each side) | 1 | 10 | 100
Sympathetic Nerve Blocks, e.g.
Cervical (stellate ganglion) | 1 | 5 | 50
Lumbar | 1 | 5 to 10 | 50 to 100
Central Neural Blocks
Epidural [Dose determined by number of dermatomes to be anesthetized (2 to 3 mL/dermatome).]
Thoracic | 1 | 20 to 30 | 200 to 300
Lumbar
Analgesia | 1 | 25 to 30 | 250 to 300
Anesthesia | 1.5 | 15 to 20 | 225 to 300
 | 2 | 10 to 15 | 200 to 300
Caudal
Obstetrical analgesia | 1 | 20 to 30 | 200 to 300
Surgical anesthesia | 1.5 | 15 to 20 | 225 to 300

THE ABOVE SUGGESTED CONCENTRATIONS AND VOLUMES SERVE ONLY AS A GUIDE. OTHER VOLUMES AND CONCENTRATIONS MAY BE USED PROVIDED THE TOTAL MAXIMUM RECOMMENDED DOSE IS NOT EXCEEDED.

Sterilization, Storage and Technical Procedures

Disinfecting agents containing heavy metals, which cause release of respective ions (mercury, zinc, copper, etc.) should not be used for skin or mucous membrane disinfection as they have been related to incidents of swelling and edema. When chemical disinfection of multi-dose vials is desired, either isopropyl alcohol (91%) or ethyl alcohol (70%) is recommended. Many commercially available brands of rubbing alcohol, as well as solutions of ethyl alcohol not of USP grade, contain denaturants which are injurious to rubber and therefore are not to be used. It is recommended that chemical disinfection be accomplished by wiping the vial stopper thoroughly with cotton or gauze that has been moistened with the recommended alcohol just prior to use.

HOW SUPPLIED

Lidocaine Hydrochloride Injection, USP is supplied as follows:

Unit of Sale | Concentration | Each
Multiple-dose:
NDC 0409-4277-02; Tray of 25 | 2%; 1000 mg/50 mL (20 mg/mL) | NDC 0409-4277-17 Plastic Fliptop Vial

STORAGE AND HANDLING

Store at 20 to 25°C (68 to 77°F). [see USP Controlled Room Temperature.]

Lidocaine Hydrochloride Injection, USP solutions packaged in ampuls and glass teartop vials may be autoclaved one time only. Autoclave at 15 pounds pressure, 121°C (250°F) for 15 minutes. DO NOT AUTOCLAVE PRODUCT IN PLASTIC VIALS.

LAB-1118-3.0
05/2018

Bupivacaine Hydrochloride Injection, USP

Rx only

1.1 DESCRIPTION

Bupivacaine hydrochloride USP is 2-Piperidinecarboxamide, 1-butyl-N-(2,6-dimethylphenyl)-, monohydrochloride, monohydrate, a white, odorless, crystalline powder that is freely soluble in 95 percent ethanol, soluble in water, and slightly soluble in chloroform or acetone. It has the following structural formula:

Bupivacaine hydrochloride injection USP is available in sterile isotonic solution for injection via local infiltration, peripheral nerve block, and caudal and lumbar epidural blocks. Solution of bupivacaine hydrochloride injection USP may be autoclaved. Solution is clear and colorless.

Bupivacaine is related chemically and pharmacologically to the aminoacyl local anesthetics. It is a homologue of mepivacaine and is chemically related to lidocaine. All three of these anesthetics contain an amide linkage between the aromatic nucleus and the amino, or piperidine group. They differ in this respect from the procaine-type local anesthetics, which have an ester linkage.

Bupivacaine hydrochloride injection USP — Sterile isotonic solution containing sodium chloride. In multiple-dose vials, each mL also contains 1 mg methylparaben as antiseptic preservative. The pH of the solution is adjusted to between 4 and 6.5 with sodium hydroxide or hydrochloric acid.

1.2 CLINICAL PHARMACOLOGY

Local anesthetics block the generation and the conduction of nerve impulses, presumably by increasing the threshold for electrical excitation in the nerve, by slowing the propagation of the nerve impulse, and by reducing the rate of rise of the action potential. In general, the progression of anesthesia is related to the diameter, myelination, and conduction velocity of affected nerve fibers. Clinically, the order of loss of nerve function is as follows: (1) pain, (2) temperature, (3) touch, (4) proprioception, and (5) skeletal muscle tone.

Systemic absorption of local anesthetics produces effects on the cardiovascular and central nervous systems (CNS). At blood concentrations achieved with normal therapeutic doses, changes in cardiac conduction, excitability, refractoriness, contractility, and peripheral vascular resistance are minimal. However, toxic blood concentrations depress cardiac conduction and excitability, which may lead to atrioventricular block, ventricular arrhythmias, and cardiac arrest, sometimes resulting in fatalities. In addition, myocardial contractility is depressed and peripheral vasodilation occurs, leading to decreased cardiac output and arterial blood pressure. Recent clinical reports and animal research suggest that these cardiovascular changes are more likely to occur after unintended intravascular injection of bupivacaine. Therefore, incremental dosing is necessary.

Following systemic absorption, local anesthetics can produce central nervous system stimulation, depression, or both. Apparent central stimulation is manifested as restlessness, tremors and shivering progressing to convulsions, followed by depression and coma progressing ultimately to respiratory arrest. However, the local anesthetics have a primary depressant effect on the medulla and on higher centers. The depressed stage may occur without a prior excited state.

1.2.1 Pharmacokinetics

The rate of systemic absorption of local anesthetics is dependent upon the total dose and concentration of drug administered, the route of administration, the vascularity of the administration site, and the presence or absence of epinephrine in the anesthetic solution. A dilute concentration of epinephrine (1:200,000 or 5 mcg/mL) usually reduces the rate of absorption and peak plasma concentration of bupivacaine, permitting the use of moderately larger total doses and sometimes prolonging the duration of action.

The onset of action with bupivacaine is rapid and anesthesia is long lasting. The duration of anesthesia is significantly longer with bupivacaine than with any other commonly used local anesthetic. It has also been noted that there is a period of analgesia that persists after the return of sensation, during which time the need for strong analgesics is reduced.

Local anesthetics are bound to plasma proteins in varying degrees. Generally, the lower the plasma concentration of drug the higher the percentage of drug bound to plasma proteins.

Local anesthetics appear to cross the placenta by passive diffusion. The rate and degree of diffusion is governed by (1) the degree of plasma protein binding, (2) the degree of ionization, and (3) the degree of lipid solubility. Fetal/maternal ratios of local anesthetics appear to be inversely related to the degree of plasma protein binding, because only the free, unbound drug is available for placental transfer. Bupivacaine with a high protein binding capacity (95%) has a low fetal/maternal ratio (0.2 to 0.4). The extent of placental transfer is also determined by the degree of ionization and lipid solubility of the drug. Lipid soluble, nonionized drugs readily enter the fetal blood from the maternal circulation.

Depending upon the route of administration, local anesthetics are distributed to some extent to all body tissues, with high concentrations found in highly perfused organs such as the liver, lungs, heart, and brain.

Pharmacokinetic studies on the plasma profile of bupivacaine after direct intravenous injection suggest a three-compartment open model. The first compartment is represented by the rapid intravascular distribution of the drug. The second compartment represents the equilibration of the drug throughout the highly perfused organs such as the brain, myocardium, lungs, kidneys, and liver. The third compartment represents an equilibration of the drug with poorly perfused tissues, such as muscle and fat. The elimination of drug from tissue distribution depends largely upon the ability of binding sites in the circulation to carry it to the liver where it is metabolized.

After injection of bupivacaine hydrochloride for caudal, epidural, or peripheral nerve block in man, peak levels of bupivacaine in the blood are reached in 30 to 45 minutes, followed by a decline to insignificant levels during the next three to six hours.

Various pharmacokinetic parameters of the local anesthetics can be significantly altered by the presence of hepatic or renal disease, addition of epinephrine, factors affecting urinary pH, renal blood flow, the route of drug administration, and the age of the patient. The half-life of bupivacaine in adults is 2.7 hours and in neonates 8.1 hours.

In clinical studies, elderly patients reached the maximal spread of analgesia and maximal motor blockade more rapidly than younger patients. Elderly patients also exhibited higher peak plasma concentrations following administration of this product. The total plasma clearance was decreased in these patients.

Amide-type local anesthetics such as bupivacaine are metabolized primarily in the liver via conjugation with glucuronic acid. Patients with hepatic disease, especially those with severe hepatic disease, may be more susceptible to the potential toxicities of the amide-type local anesthetics. Pipecoloxylidine is the major metabolite of bupivacaine.

The kidney is the main excretory organ for most local anesthetics and their metabolites. Urinary excretion is affected by urinary perfusion and factors affecting urinary pH. Only 6% of bupivacaine is excreted unchanged in the urine.

When administered in recommended doses and concentrations, bupivacaine hydrochloride does not ordinarily produce irritation or tissue damage and does not cause methemoglobinemia.

1.3 INDICATIONS AND USAGE

Bupivacaine hydrochloride injection USP is indicated for the production of local or regional anesthesia or analgesia for surgery, diagnostic and therapeutic procedures, and for obstetrical procedures. Only the 0.25% and 0.5% concentrations are indicated for obstetrical anesthesia. (See WARNINGS.)

Experience with nonobstetrical surgical procedures in pregnant patients is not sufficient to recommend use of 0.75% concentration of bupivacaine hydrochloride injection USP in these patients.

Bupivacaine hydrochloride injection USP is not recommended for intravenous regional anesthesia (Bier Block). See WARNINGS.

The routes of administration and indicated bupivacaine hydrochloride injection USP concentrations are:

- local infiltration 0.25%
- peripheral nerve block 0.25% and 0.5%
- retrobulbar block 0.75%
- sympathetic block 0.25%
- lumbar epidural 0.25%, 0.5%, and 0.75% (0.75% not for obstetrical anesthesia)
- caudal 0.25% and 0.5%
- epidural test dose (see PRECAUTIONS)

(See DOSAGE AND ADMINISTRATION for additional information.)

Standard textbooks should be consulted to determine the accepted procedures and techniques for the administration of bupivacaine hydrochloride injection USP.

1.4 CONTRAINDICATIONS

Bupivacaine hydrochloride injection is contraindicated in obstetrical paracervical block anesthesia. Its use in this technique has resulted in fetal bradycardia and death.

Bupivacaine hydrochloride injection is contraindicated in patients with a known hypersensitivity to it or to any local anesthetic agent of the amide-type or to other components of bupivacaine hydrochloride injection solutions.

1.5 WARNINGS

BOXED WARNING

THE 0.75% CONCENTRATION OF BUPIVACAINE HYDROCHLORIDE IS NOT RECOMMENDED FOR OBSTETRICAL ANESTHESIA. THERE HAVE BEEN REPORTS OF CARDIAC ARREST WITH DIFFICULT RESUSCITATION OR DEATH DURING USE OF BUPIVACAINE HYDROCHLORIDE FOR EPIDURAL ANESTHESIA IN OBSTETRICAL PATIENTS. IN MOST CASES, THIS HAS FOLLOWED USE OF THE 0.75% CONCENTRATION. RESUSCITATION HAS BEEN DIFFICULT OR IMPOSSIBLE DESPITE APPARENTLY ADEQUATE PREPARATION AND APPROPRIATE MANAGEMENT. CARDIAC ARREST HAS OCCURRED AFTER CONVULSIONS RESULTING FROM SYSTEMIC TOXICITY, PRESUMABLY FOLLOWING UNINTENTIONAL INTRAVASCULAR INJECTION. THE 0.75% CONCENTRATION SHOULD BE RESERVED FOR SURGICAL PROCEDURES WHERE A HIGH DEGREE OF MUSCLE RELAXATION AND PROLONGED EFFECT ARE NECESSARY.

LOCAL ANESTHETICS SHOULD ONLY BE EMPLOYED BY CLINICIANS WHO ARE WELL VERSED IN DIAGNOSIS AND MANAGEMENT OF DOSE-RELATED TOXICITY AND OTHER ACUTE EMERGENCIES WHICH MIGHT ARISE FROM THE BLOCK TO BE EMPLOYED, AND THEN ONLY AFTER INSURING THE IMMEDIATE AVAILABILITY OF OXYGEN, OTHER RESUSCITATIVE DRUGS, CARDIOPULMONARY RESUSCITATIVE EQUIPMENT, AND THE PERSONNEL RESOURCES NEEDED FOR PROPER MANAGEMENT OF TOXIC REACTIONS AND RELATED EMERGENCIES. (See also ADVERSE REACTIONS, PRECAUTIONS, and OVERDOSAGE.) DELAY IN PROPER MANAGEMENT OF DOSE-RELATED TOXICITY, UNDERVENTILATION FROM ANY CAUSE, AND/OR ALTERED SENSITIVITY MAY LEAD TO THE DEVELOPMENT OF ACIDOSIS, CARDIAC ARREST AND, POSSIBLY, DEATH.

Local anesthetic solutions containing antimicrobial preservatives, i.e., those supplied in multiple-dose vials, should not be used for epidural or caudal anesthesia because safety has not been established with regard to intrathecal injection, either intentionally or unintentionally, of such preservatives.

Intra-articular infusions of local anesthetics following arthroscopic and other surgical procedures is an unapproved use, and there have been post-marketing reports of chondrolysis in patients receiving such infusions. The majority of reported cases of chondrolysis have involved the shoulder joint; cases of gleno-humeral chondrolysis have been described in pediatric and adult patients following intra-articular infusions of local anesthetics with and without epinephrine for periods of 48 to 72 hours. There is insufficient information to determine whether shorter infusion periods are not associated with these findings. The time of onset of symptoms, such as joint pain, stiffness and loss of motion can be variable, but may begin as early as the 2nd month after surgery. Currently, there is no effective treatment for chondrolysis; patients who experienced chondrolysis have required additional diagnostic and therapeutic procedures and some required arthroplasty or shoulder replacement.

It is essential that aspiration for blood or cerebrospinal fluid (where applicable) be done prior to injecting any local anesthetic, both the original dose and all subsequent doses, to avoid intravascular or subarachnoid injection. However, a negative aspiration does not ensure against an intravascular or subarachnoid injection.

Until further experience is gained in pediatric patients younger than 12 years, administration of bupivacaine hydrochloride in this age group is not recommended.

Mixing or the prior or intercurrent use of any other local anesthetic with bupivacaine hydrochloride cannot be recommended because of insufficient data on the clinical use of such mixtures.

There have been reports of cardiac arrest and death during the use of bupivacaine hydrochloride for intravenous regional anesthesia (Bier Block). Information on safe dosages and techniques of administration of bupivacaine hydrochloride in this procedure is lacking. Therefore, bupivacaine hydrochloride is not recommended for use in this technique.

1.6 PRECAUTIONS

1.6.1 General

The safety and effectiveness of local anesthetics depend on proper dosage, correct technique, adequate precautions, and readiness for emergencies. Resuscitative equipment, oxygen, and other resuscitative drugs should be available for immediate use. (See WARNINGS, ADVERSE REACTIONS, and OVERDOSAGE.) During major regional nerve blocks, the patient should have IV fluids running via an indwelling catheter to assure a functioning intravenous pathway. The lowest dosage of local anesthetic that results in effective anesthesia should be used to avoid high plasma levels and serious adverse effects. The rapid injection of a large volume of local anesthetic solution should be avoided and fractional (incremental) doses should be used when feasible.

1.6.2 Epidural Anesthesia

During epidural administration of bupivacaine hydrochloride, 0.5% and 0.75% solutions should be administered in incremental doses of 3 mL to 5 mL with sufficient time between doses to detect toxic manifestations of unintentional intravascular or intrathecal injection. Injections should be made slowly, with frequent aspirations before and during the injection to avoid intravascular injection. Syringe aspirations should also be performed before and during each supplemental injection in continuous (intermittent) catheter techniques. An intravascular injection is still possible even if aspirations for blood are negative.

During the administration of epidural anesthesia, it is recommended that a test dose be administered initially and the effects monitored before the full dose is given. When using a “continuous” catheter technique, test doses should be given prior to both the original and all reinforcing doses, because plastic tubing in the epidural space can migrate into a blood vessel or through the dura. When clinical conditions permit, the test dose should contain epinephrine (10 mcg to 15 mcg has been suggested) to serve as a warning of unintended intravascular injection. If injected into a blood vessel, this amount of epinephrine is likely to produce a transient “epinephrine response” within 45 seconds, consisting of an increase in heart rate and/or systolic blood pressure, circumoral pallor, palpitations, and nervousness in the unsedated patient. The sedated patient may exhibit only a pulse rate increase of 20 or more beats per minute for 15 or more seconds. Therefore, following the test dose, the heart rate should be monitored for a heart rate increase. Patients on beta-blockers may not manifest changes in heart rate, but blood pressure monitoring can detect a transient rise in systolic blood pressure. The test dose should also contain 10 mg to 15 mg of bupivacaine hydrochloride or an equivalent amount of another local anesthetic to detect an unintended intrathecal administration. This will be evidenced within a few minutes by signs of spinal block (e.g., decreased sensation of the buttocks, paresis of the legs, or, in the sedated patient, absent knee jerk). The Test Dose formulation of bupivacaine hydrochloride contains 15 mg of bupivacaine and 15 mcg of epinephrine in a volume of 3 mL. An intravascular or subarachnoid injection is still possible even if results of the test dose are negative. The test dose itself may produce a systemic toxic reaction, high spinal or epinephrine-induced cardiovascular effects.

Injection of repeated doses of local anesthetics may cause significant increases in plasma levels with each repeated dose due to slow accumulation of the drug or its metabolites, or to slow metabolic degradation. Tolerance to elevated blood levels varies with the status of the patient. Debilitated, elderly patients and acutely ill patients should be given reduced doses commensurate with their age and physical status. Local anesthetics should also be used with caution in patients with hypotension or heartblock.

Careful and constant monitoring of cardiovascular and respiratory (adequacy of ventilation) vital signs and the patient’s state of consciousness should be performed after each local anesthetic injection. It should be kept in mind at such times that restlessness, anxiety, incoherent speech, lightheadedness, numbness and tingling of the mouth and lips, metallic taste, tinnitus, dizziness, blurred vision, tremors, twitching, depression, or drowsiness may be early warning signs of central nervous system toxicity.

Local anesthetic solutions containing a vasoconstrictor should be used cautiously and in carefully restricted quantities in areas of the body supplied by end arteries or having otherwise compromised blood supply such as digits, nose, external ear, or penis. Patients with hypertensive vascular disease may exhibit exaggerated vasoconstrictor response. Ischemic injury or necrosis may result.

Because amide-local anesthetics such as bupivacaine are metabolized by the liver, these drugs, especially repeat doses, should be used cautiously in patients with hepatic disease. Patients with severe hepatic disease, because of their inability to metabolize local anesthetics normally, are at a greater risk of developing toxic plasma concentrations. Local anesthetics should also be used with caution in patients with impaired cardiovascular function because they may be less able to compensate for functional changes associated with the prolongation of AV conduction produced by these drugs.

Serious dose-related cardiac arrhythmias may occur if preparations containing a vasoconstrictor such as epinephrine are employed in patients during or following the administration of potent inhalation anesthetics. In deciding whether to use these products concurrently in the same patient, the combined action of both agents upon the myocardium, the concentration and volume of vasoconstrictor used, and the time since injection, when applicable, should be taken into account.

Many drugs used during the conduct of anesthesia are considered potential triggering agents for familial malignant hyperthermia. Because it is not known whether amide-type local anesthetics may trigger this reaction and because the need for supplemental general anesthesia cannot be predicted in advance, it is suggested that a standard protocol for management should be available. Early unexplained signs of tachycardia, tachypnea, labile blood pressure, and metabolic acidosis may precede temperature elevation. Successful outcome is dependent on early diagnosis, prompt discontinuance of the suspect triggering agent(s) and prompt institution of treatment, including oxygen therapy, indicated supportive measures and dantrolene. (Consult dantrolene sodium intravenous package insert before using.)

1.6.3 Use in Head and Neck Area

Small doses of local anesthetics injected into the head and neck area, including retrobulbar, and stellate ganglion blocks, may produce adverse reactions similar to systemic toxicity seen with unintentional intravascular injections of larger doses. The injection procedures require the utmost care. Confusion, convulsions, respiratory depression, and/or respiratory arrest, and cardiovascular stimulation or depression have been reported. These reactions may be due to intra-arterial injection of the local anesthetic with retrograde flow to the cerebral circulation. They may also be due to puncture of the dural sheath of the optic nerve during retrobulbar block with diffusion of any local anesthetic along the subdural space to the midbrain. Patients receiving these blocks should have their circulation and respiration monitored and be constantly observed. Resuscitative equipment and personnel for treating adverse reactions should be immediately available. Dosage recommendations should not be exceeded. (See DOSAGE AND ADMINISTRATION.)

1.6.4 Use in Ophthalmic Surgery

Clinicians who perform retrobulbar blocks should be aware that there have been reports of respiratory arrest following local anesthetic injection. Prior to retrobulbar block, as with all other regional procedures, the immediate availability of equipment, drugs, and personnel to manage respiratory arrest or depression, convulsions, and cardiac stimulation or depression should be assured (see also WARNINGS and Use in Head and Neck Area, above). As with other anesthetic procedures, patients should be constantly monitored following ophthalmic blocks for signs of these adverse reactions, which may occur following relatively low total doses.

A concentration of 0.75% bupivacaine is indicated for retrobulbar block; however, this concentration is not indicated for any other peripheral nerve block, including the facial nerve, and not indicated for local infiltration, including the conjunctiva (see INDICATIONS AND USAGE and PRECAUTIONS, General). Mixing bupivacaine hydrochloride with other local anesthetics is not recommended because of insufficient data on the clinical use of such mixtures.

When bupivacaine hydrochloride 0.75% is used for retrobulbar block, complete corneal anesthesia usually precedes onset of clinically acceptable external ocular muscle akinesia. Therefore, presence of akinesia rather than anesthesia alone should determine readiness of the patient for surgery.

1.6.5 Information for Patients

When appropriate, patients should be informed in advance that they may experience temporary loss of sensation and motor activity, usually in the lower half of the body, following proper administration of caudal or epidural anesthesia. Also, when appropriate, the physician should discuss other information including adverse reactions in the package insert of bupivacaine hydrochloride.

1.6.6 Clinically Significant Drug Interactions

The administration of local anesthetic solutions containing epinephrine or norepinephrine to patients receiving monoamine oxidase inhibitors or tricyclic antidepressants may produce severe, prolonged hypertension. Concurrent use of these agents should generally be avoided. In situations when concurrent therapy is necessary, careful patient monitoring is essential.

Concurrent administration of vasopressor drugs and of ergot-type oxytocic drugs may cause severe, persistent hypertension or cerebrovascular accidents.

Phenothiazines and butyrophenones may reduce or reverse the pressor effect of epinephrine.

1.6.7 Carcinogenesis, Mutagenesis, Impairment of Fertility

Long-term studies in animals to evaluate the carcinogenic potential of bupivacaine hydrochloride have not been conducted. The mutagenic potential and the effect on fertility of bupivacaine hydrochloride have not been determined.

1.6.8 Pregnancy Category C

There are no adequate and well-controlled studies in pregnant women. Bupivacaine hydrochloride should be used during pregnancy only if the potential benefit justifies the potential risk to the fetus. Bupivacaine hydrochloride produced developmental toxicity when administered subcutaneously to pregnant rats and rabbits at clinically relevant doses. This does not exclude the use of bupivacaine hydrochloride at term for obstetrical anesthesia or analgesia. (See Labor and Delivery.)

Bupivacaine hydrochloride was administered subcutaneously to rats at doses of 4.4, 13.3, & 40 mg/kg and to rabbits at doses of 1.3, 5.8, & 22.2 mg/kg during the period of organogenesis (implantation to closure of the hard palate). The high doses are comparable to the daily maximum recommended human dose (MRHD) of 400 mg/day on a mg/m^2 body surface area (BSA) basis. No embryo-fetal effects were observed in rats at the high dose which caused increased maternal lethality. An increase in embryo-fetal deaths was observed in rabbits at the high dose in the absence of maternal toxicity with the fetal No Observed Adverse Effect Level representing approximately 1/5th the MRHD on a BSA basis.

In a rat pre- and post-natal development study (dosing from implantation through weaning) conducted at subcutaneous doses of 4.4, 13.3, & 40 mg/kg mg/kg/day, decreased pup survival was observed at the high dose. The high dose is comparable to the daily MRHD of 400 mg/day on a BSA basis.

1.6.9 Labor and Delivery

SEE BOXED WARNING REGARDING OBSTETRlCAL USE OF 0.75% BUPIVACAINE HYDROCHLORIDE.

Bupivacaine hydrochloride is contraindicated for obstetrical paracervical block anesthesia.

Local anesthetics rapidly cross the placenta, and when used for epidural, caudal, or pudendal block anesthesia, can cause varying degrees of maternal, fetal, and neonatal toxicity. (See CLINICAL PHARMACOLOGY, Pharmacokinetics.) The incidence and degree of toxicity depend upon the procedure performed, the type, and amount of drug used, and the technique of drug administration. Adverse reactions in the parturient, fetus, and neonate involve alterations of the central nervous system, peripheral vascular tone, and cardiac function.

Maternal hypotension has resulted from regional anesthesia. Local anesthetics produce vasodilation by blocking sympathetic nerves. Elevating the patient’s legs and positioning her on her left side will help prevent decreases in blood pressure. The fetal heart rate also should be monitored continuously and electronic fetal monitoring is highly advisable.

Epidural, caudal, or pudendal anesthesia may alter the forces of parturition through changes in uterine contractility or maternal expulsive efforts. Epidural anesthesia has been reported to prolong the second stage of labor by removing the parturient’s reflex urge to bear down or by interfering with motor function. The use of obstetrical anesthesia may increase the need for forceps assistance.

The use of some local anesthetic drug products during labor and delivery may be followed by diminished muscle strength and tone for the first day or two of life. This has not been reported with bupivacaine.

It is extremely important to avoid aortocaval compression by the gravid uterus during administration of regional block to parturients. To do this, the patient must be maintained in the left lateral decubitus position or a blanket roll or sandbag may be placed beneath the right hip and gravid uterus displaced to the left.

1.6.10 Nursing Mothers

Bupivacaine has been reported to be excreted in human milk suggesting that the nursing infant could be theoretically exposed to a dose of the drug. Because of the potential for serious adverse reactions in nursing infants from bupivacaine, a decision should be made whether to discontinue nursing or not administer bupivacaine, taking into account the importance of the drug to the mother.

1.6.11 Pediatric Use

Until further experience is gained in pediatric patients younger than 12 years, administration of bupivacaine hydrochloride in this age group is not recommended. Continuous infusions of bupivacaine in children have been reported to result in high systemic levels of bupivacaine and seizures; high plasma levels may also be associated with cardiovascular abnormalities. (See WARNINGS, PRECAUTIONS, and OVERDOSAGE.)

1.6.12 Geriatric Use

Patients over 65 years, particularly those with hypertension, may be at increased risk for developing hypotension while undergoing anesthesia with bupivacaine hydrochloride. (See ADVERSE REACTIONS.)

Elderly patients may require lower doses of bupivacaine hydrochloride. (See PRECAUTIONS, Epidural Anesthesia and DOSAGE AND ADMINISTRATION.)

In clinical studies, differences in various pharmacokinetic parameters have been observed between elderly and younger patients. (See CLINICAL PHARMACOLOGY.)

This product is known to be substantially excreted by the kidney, and the risk of toxic reactions to this drug may be greater in patients with impaired renal function. Because elderly patients are more likely to have decreased renal function, care should be taken in dose selection, and it may be useful to monitor renal function. (See CLINICAL PHARMACOLOGY.)

1.7 ADVERSE REACTIONS

Reactions to bupivacaine hydrochloride are characteristic of those associated with other amide-type local anesthetics. A major cause of adverse reactions to this group of drugs is excessive plasma levels, which may be due to overdosage, unintentional intravascular injection, or slow metabolic degradation.

The most commonly encountered acute adverse experiences which demand immediate counter-measures are related to the central nervous system and the cardiovascular system. These adverse experiences are generally dose related and due to high plasma levels which may result from overdosage, rapid absorption from the injection site, diminished tolerance, or from unintentional intravascular injection of the local anesthetic solution. In addition to systemic dose-related toxicity, unintentional subarachnoid injection of drug during the intended performance of caudal or lumbar epidural block or nerve blocks near the vertebral column (especially in the head and neck region) may result in underventilation or apnea (“Total or High Spinal”). Also, hypotension due to loss of sympathetic tone and respiratory paralysis or underventilation due to cephalad extension of the motor level of anesthesia may occur. This may lead to secondary cardiac arrest if untreated. Patients over 65 years, particularly those with hypertension, may be at increased risk for experiencing the hypotensive effects of bupivacaine hydrochloride. Factors influencing plasma protein binding, such as acidosis, systemic diseases which alter protein production, or competition of other drugs for protein binding sites, may diminish individual tolerance.

1.7.1 Central Nervous System Reactions

These are characterized by excitation and/or depression. Restlessness, anxiety, dizziness, tinnitus, blurred vision, or tremors may occur, possibly proceeding to convulsions. However, excitement may be transient or absent, with depression being the first manifestation of an adverse reaction. This may quickly be followed by drowsiness merging into unconsciousness and respiratory arrest. Other central nervous system effects may be nausea, vomiting, chills, and constriction of the pupils.

The incidence of convulsions associated with the use of local anesthetics varies with the procedure used and the total dose administered. In a survey of studies of epidural anesthesia, overt toxicity progressing to convulsions occurred in approximately 0.1% of local anesthetic administrations.

1.7.2 Cardiovascular System Reactions

High doses or unintentional intravascular injection may lead to high plasma levels and related depression of the myocardium, decreased cardiac output, heartblock, hypotension, bradycardia, ventricular arrhythmias, including ventricular tachycardia and ventricular fibrillation, and cardiac arrest. (See WARNINGS, PRECAUTIONS, and OVERDOSAGE.)

1.7.3 Allergic

Allergic-type reactions are rare and may occur as a result of sensitivity to the local anesthetic or to other formulation ingredients, such as the antimicrobial preservative methylparaben contained in multiple-dose vials. These reactions are characterized by signs such as urticaria, pruritus, erythema, angioneurotic edema (including laryngeal edema), tachycardia, sneezing, nausea, vomiting, dizziness, syncope, excessive sweating, elevated temperature, and possibly, anaphylactoid-like symptomatology (including severe hypotension). Cross sensitivity among members of the amide-type local anesthetic group has been reported. The usefulness of screening for sensitivity has not been definitely established.

1.7.4 Neurologic

The incidences of adverse neurologic reactions associated with the use of local anesthetics may be related to the total dose of local anesthetic administered and are also dependent upon the particular drug used, the route of administration, and the physical status of the patient. Many of these effects may be related to local anesthetic techniques, with or without a contribution from the drug.

In the practice of caudal or lumbar epidural block, occasional unintentional penetration of the subarachnoid space by the catheter or needle may occur. Subsequent adverse effects may depend partially on the amount of drug administered intrathecally and the physiological and physical effects of a dural puncture. A high spinal is characterized by paralysis of the legs, loss of consciousness, respiratory paralysis, and bradycardia.

Neurologic effects following epidural or caudal anesthesia may include spinal block of varying magnitude (including high or total spinal block); hypotension secondary to spinal block; urinary retention; fecal and urinary incontinence; loss of perineal sensation and sexual function; persistent anesthesia, paresthesia, weakness, paralysis of the lower extremities and loss of sphincter control all of which may have slow, incomplete, or no recovery; headache; backache; septic meningitis; meningismus; slowing of labor; increased incidence of forceps delivery; and cranial nerve palsies due to traction on nerves from loss of cerebrospinal fluid.

Neurologic effects following other procedures or routes of administration may include persistent anesthesia, paresthesia, weakness, paralysis, all of which may have slow, incomplete, or no recovery.

1.8 OVERDOSAGE

Acute emergencies from local anesthetics are generally related to high plasma levels encountered during therapeutic use of local anesthetics or to unintended subarachnoid injection of local anesthetic solution. (See ADVERSE REACTIONS, WARNINGS, and PRECAUTIONS.)

1.8.1 Management of Local Anesthetic Emergencies

The first consideration is prevention, best accomplished by careful and constant monitoring of cardiovascular and respiratory vital signs and the patient’s state of consciousness after each local anesthetic injection. At the first sign of change, oxygen should be administered.

The first step in the management of systemic toxic reactions, as well as underventilation or apnea due to unintentional subarachnoid injection of drug solution, consists of immediate attention to the establishment and maintenance of a patent airway and effective assisted or controlled ventilation with 100% oxygen with a delivery system capable of permitting immediate positive airway pressure by mask. This may prevent convulsions if they have not already occurred.

If necessary, use drugs to control the convulsions. A 50 mg to 100 mg bolus IV injection of succinylcholine will paralyze the patient without depressing the central nervous or cardiovascular systems and facilitate ventilation. A bolus IV dose of 5 mg to 10 mg of diazepam or 50 mg to 100 mg of thiopental will permit ventilation and counteract central nervous system stimulation, but these drugs also depress central nervous system, respiratory, and cardiac function, add to postictal depression and may result in apnea. Intravenous barbiturates, anticonvulsant agents, or muscle relaxants should only be administered by those familiar with their use. Immediately after the institution of these ventilatory measures, the adequacy of the circulation should be evaluated. Supportive treatment of circulatory depression may require administration of intravenous fluids, and when appropriate, a vasopressor dictated by the clinical situation (such as ephedrine or epinephrine to enhance myocardial contractile force).

Endotracheal intubation, employing drugs and techniques familiar to the clinician, may be indicated after initial administration of oxygen by mask if difficulty is encountered in the maintenance of a patent airway, or if prolonged ventilatory support (assisted or controlled) is indicated.

Recent clinical data from patients experiencing local anesthetic-induced convulsions demonstrated rapid development of hypoxia, hypercarbia, and acidosis with bupivacaine within a minute of the onset of convulsions. These observations suggest that oxygen consumption and carbon dioxide production are greatly increased during local anesthetic convulsions and emphasize the importance of immediate and effective ventilation with oxygen which may avoid cardiac arrest.

If not treated immediately, convulsions with simultaneous hypoxia, hypercarbia, and acidosis plus myocardial depression from the direct effects of the local anesthetic may result in cardiac arrhythmias, bradycardia, asystole, ventricular fibrillation, or cardiac arrest. Respiratory abnormalities, including apnea, may occur. Underventilation or apnea due to unintentional subarachnoid injection of local anesthetic solution may produce these same signs and also lead to cardiac arrest if ventilatory support is not instituted. If cardiac arrest should occur, successful outcome may require prolonged resuscitative efforts.

The supine position is dangerous in pregnant women at term because of aortocaval compression by the gravid uterus. Therefore during treatment of systemic toxicity, maternal hypotension or fetal bradycardia following regional block, the parturient should be maintained in the left lateral decubitus position if possible, or manual displacement of the uterus off the great vessels be accomplished.

The mean seizure dosage of bupivacaine in rhesus monkeys was found to be 4.4 mg/kg with mean arterial plasma concentration of 4.5 mcg/mL. The intravenous and subcutaneous LD50 in mice is 6 mg/kg to 8 mg/kg and 38 mg/kg to 54 mg/kg respectively.

1.9 DOSAGE AND ADMINISTRATION

NOTE: The products accompanying this insert do not contain epinephrine.

The dose of any local anesthetic administered varies with the anesthetic procedure, the area to be anesthetized, the vascularity of the tissues, the number of neuronal segments to be blocked, the depth of anesthesia and degree of muscle relaxation required, the duration of anesthesia desired, individual tolerance, and the physical condition of the patient. The smallest dose and concentration required to produce the desired result should be administered. Dosages of bupivacaine hydrochloride injection should be reduced for elderly and/or debilitated patients and patients with cardiac and/or liver disease. The rapid injection of a large volume of local anesthetic solution should be avoided and fractional (incremental) doses should be used when feasible.

For specific techniques and procedures, refer to standard textbooks.

There have been adverse event reports of chondrolysis in patients receiving intra-articular infusions of local anesthetics following arthroscopic and other surgical procedures. Bupivacaine hydrochloride injection is not approved for this use (see WARNINGS and DOSAGE AND ADMINISTRATION).

In recommended doses, bupivacaine hydrochloride produces complete sensory block, but the effect on motor function differs among the three concentrations.

0.25% — when used for caudal, epidural, or peripheral nerve block, produces incomplete motor block. Should be used for operations in which muscle relaxation is not important, or when another means of providing muscle relaxation is used concurrently. Onset of action may be slower than with the 0.5% or 0.75% solutions.

0.5% — provides motor blockade for caudal, epidural, or nerve block, but muscle relaxation may be inadequate for operations in which complete muscle relaxation is essential.

0.75% — produces complete motor block. Most useful for epidural block in abdominal operations requiring complete muscle relaxation, and for retrobulbar anesthesia. Not for obstetrical anesthesia.

The duration of anesthesia with bupivacaine hydrochloride injection is such that for most indications, a single dose is sufficient.

Maximum dosage limit must be individualized in each case after evaluating the size and physical status of the patient, as well as the usual rate of systemic absorption from a particular injection site. Most experience to date is with single doses of bupivacaine hydrochloride injection up to 225 mg with epinephrine 1:200,000 and 175 mg without epinephrine; more or less drug may be used depending on individualization of each case.

These doses may be repeated up to once every three hours. In clinical studies to date, total daily doses have been up to 400 mg. Until further experience is gained, this dose should not be exceeded in 24 hours. The duration of anesthetic effect may be prolonged by the addition of epinephrine.

The dosages in Table 1 have generally proved satisfactory and are recommended as a guide for use in the average adult. These dosages should be reduced for elderly or debilitated patients. Until further experience is gained, bupivacaine hydrochloride injection is not recommended for pediatric patients younger than 12 years. Bupivacaine hydrochloride injection is contraindicated for obstetrical paracervical blocks, and is not recommended for intravenous regional anesthesia (Bier Block).

1.9.1 Use in Epidural Anesthesia

During epidural administration of bupivacaine hydrochloride injection, 0.5% and 0.75% solutions should be administered in incremental doses of 3 mL to 5 mL with sufficient time between doses to detect toxic manifestations of unintentional intravascular or intrathecal injection. In obstetrics, only the 0.5% and 0.25% concentrations should be used; incremental doses of 3 mL to 5 mL of the 0.5% solution not exceeding 50 mg to 100 mg at any dosing interval are recommended. Repeat doses should be preceded by a test dose containing epinephrine if not contraindicated. Use only the single-dose ampuls and single-dose vials for caudal or epidural anesthesia; the multiple-dose vials contain a preservative and therefore should not be used for these procedures.

Test Dose for Caudal and Lumbar Epidural Blocks

See PRECAUTIONS

This product should be inspected visually for particulate matter and discoloration prior to administration whenever solution and container permit. Solutions which are discolored or which contain particulate matter should not be administered.

Table 1. Recommended Concentrations and Doses of Bupivacaine Hydrochloride Injection
Type of Block | Conc. | Each Dose |  | Motor Block^1
Type of Block | Conc. | (mL) | (mg) | Motor Block^1
Local infiltration | 0.25%^4 | up to max. | up to max. | --
Epidural | 0.75%^2,4 | 10 to 20 | 75 to 150 | complete
 | 0.5%^4 | 10 to 20 | 50 to 100 | moderate to complete
 | 0.25%^4 | 10 to 20 | 25 to 50 | partial to moderate
Caudal | 0.5%^4 | 15 to 30 | 75 to 150 | moderate to complete
 | 0.25%^4 | 15 to 30 | 37.5 to 75 | moderate
Peripheral nerves | 0.5%^4 | 5 to max. | 25 to max. | moderate to complete
 | 0.25%^4 | 5 to max. | 12.5 to max. | moderate to complete
Retrobulbar^3 | 0.75%^4 | 2 to 4 | 15 to 30 | complete
Sympathetic | 0.25% | 20 to 50 | 50 to 125 | --
Epidural^3 Test Dose | 0.5% w/epi | 2 to 3 | 10 to 15 (10 to 15 micrograms epinephrine) | --
^1With continuous (intermittent) techniques, repeat doses increase the degree of motor block. The first repeat dose of 0.5% may produce complete motor block. Intercostal nerve block with 0.25% may also produce complete motor block for intra-abdominal surgery.
^2 For single-dose use, not for intermittent epidural technique. Not for obstetrical anesthesia.
^3 See PRECAUTIONS.
^4 Solutions with or without epinephrine.

1.10 HOW SUPPLIED

These solutions are not for spinal anesthesia.

Bupivacaine Hydrochloride Injection USP — Solution of Bupivacaine hydrochloride injection USP may be autoclaved. Autoclave at 15-pound pressure, 121°C (250°F) for 15 minutes.

Bupivacaine Hydrochloride Injection USP is a clear, colorless, sterile isotonic solution and is available as follows:

Bupivacaine Hydrochloride Injection USP 0.25% (2.5 mg/mL)

50 mL Multiple Dose Vials in a Carton of 25 NDC 55150-249-50

Store at 20° to 25°C (68° to 77°F). [See USP Controlled Room Temperature.]

The vial stoppers are not made with natural rubber latex.

Sterile, Nonpyrogenic

Revised: June 2017

Betamethasone Sodium Phosphate and Betamethasone Acetate Injectable Suspension, USP, 6 mg/mL

30 mg/5 mL (6 mg/mL)

2.1 DESCRIPTION

Betamethasone Sodium Phosphate and Betamethasone Acetate Injectable Suspension is a sterile aqueous suspension containing 3 mg per milliliter betamethasone, as betamethasone sodium phosphate, and 3 mg per milliliter betamethasone acetate. Inactive ingredients per mL: 7.1 mg dibasic sodium phosphate anhydrous; 3.4 mg monobasic sodium phosphate monohydrate; 0.1 mg edetate disodium; and 0.2 mg benzalkonium chloride as a preservative. The pH is adjusted to between 6.8 and 7.2.

The formula for betamethasone sodium phosphate is C22H28FNa2O8P and it has a molecular weight of 516.40. Chemically, it is 9-Fluoro-11β,17,21-trihydroxy-16β-methylpregna-1,4-diene-3,20-dione 21-(disodium phosphate).

The formula for betamethasone acetate is C24H31FO6 and it has a molecular weight of 434.50. Chemically, it is 9-Fluoro-11β,17,21-trihydroxy-16β-methylpregna-1,4-diene-3,20-dione 21-acetate.

The chemical structures for betamethasone sodium phosphate and betamethasone acetate are as follows:

Betamethasone sodium phosphate is a white to practically white, odorless powder, and is hygroscopic. It is freely soluble in water and in methanol, but is practically insoluble in acetone and in chloroform.

Betamethasone acetate is a white to creamy white, odorless powder that sinters and resolidifies at about 165ºC, and remelts at about 200ºC to 220ºC with decomposition. It is practically insoluble in water, but freely soluble in acetone, and is soluble in alcohol and in chloroform.

2.2 CLINICAL PHARMACOLOGY

Glucocorticoids, naturally occurring and synthetic, are adrenocortical steroids that are readily absorbed from the gastrointestinal tract.

Naturally occurring glucocorticoids (hydrocortisone and cortisone), which also have salt-retaining properties, are used as replacement therapy in adrenocortical deficiency states. Their synthetic analogs are primarily used for their anti-inflammatory effects in disorders of many organ systems. A derivative of prednisolone, betamethasone has a 16β-methyl group that enhances the anti-inflammatory action of the molecule and reduces the sodium- and water-retaining properties of the fluorine atom bound at carbon 9.

Betamethasone sodium phosphate, a soluble ester, provides prompt activity, while betamethasone acetate is only slightly soluble and affords sustained activity.

2.3 INDICATIONS AND USAGE

When oral therapy is not feasible, the intramuscular use of Betamethasone Sodium Phosphate and Betamethasone Acetate Injectable Suspension is indicated as follows:

Allergic States Control of severe or incapacitating allergic conditions intractable to adequate trials of conventional treatment in asthma, atopic dermatitis, contact dermatitis, drug hypersensitivity reactions, perennial or seasonal allergic rhinitis, serum sickness, transfusion reactions.

Dermatologic Diseases Bullous dermatitis herpetiformis, exfoliative erythroderma, mycosis fungoides, pemphigus, severe erythema multiforme (Stevens-Johnson syndrome).

Endocrine Disorders Congenital adrenal hyperplasia, hypercalcemia associated with cancer, nonsuppurative thyroiditis.

Hydrocortisone or cortisone is the drug of choice in primary or secondary adrenocortical insufficiency. Synthetic analogs may be used in conjunction with mineralocorticoids where applicable; in infancy mineralocorticoid supplementation is of particular importance.

Gastrointestinal Diseases To tide the patient over a critical period of the disease in regional enteritis and ulcerative colitis.

Hematologic Disorders Acquired (autoimmune) hemolytic anemia, Diamond-Blackfan anemia, pure red cell aplasia, selected cases of secondary thrombocytopenia.

Miscellaneous Trichinosis with neurologic or myocardial involvement, tuberculous meningitis with subarachnoid block or impending block when used with appropriate antituberculous chemotherapy.

Neoplastic Diseases For palliative management of leukemias and lymphomas.

Nervous System Acute exacerbations of multiple sclerosis; cerebral edema associated with primary or metastatic brain tumor or craniotomy.

Ophthalmic Diseases Sympathetic ophthalmia, temporal arteritis, uveitis and ocular inflammatory conditions unresponsive to topical corticosteroids.

Renal Diseases To induce diuresis or remission of proteinuria in idiopathic nephrotic syndrome or that due to lupus erythematosus.

Respiratory Diseases Berylliosis, fulminating or disseminated pulmonary tuberculosis when used concurrently with appropriate antituberculous chemotherapy, idiopathic eosinophilic pneumonias, symptomatic sarcoidosis.

Rheumatic Disorders As adjunctive therapy for short-term administration (to tide the patient over an acute episode or exacerbation) in acute gouty arthritis; acute rheumatic carditis; ankylosing spondylitis; psoriatic arthritis; rheumatoid arthritis, including juvenile rheumatoid arthritis (selected cases may require low-dose maintenance therapy). For the treatment of dermatomyositis, polymyositis, and systemic lupus erythematosus.

The intra-articular or soft tissue administration of Betamethasone Sodium Phosphate and Betamethasone Acetate Injectable Suspension is indicated as adjunctive therapy for short-term administration (to tide the patient over an acute episode or exacerbation) in acute gouty arthritis, acute and subacute bursitis, acute nonspecific tenosynovitis, epicondylitis, rheumatoid arthritis, synovitis of osteoarthritis.

The intralesional administration of Betamethasone Sodium Phosphate and Betamethasone Acetate Injectable Suspension is indicated for alopecia areata; discoid lupus erythematosus; keloids; localized hypertrophic, infiltrated, inflammatory lesions of granuloma annulare, lichen planus, lichen simplex chronicus (neurodermatitis), and psoriatic plaques; necrobiosis lipoidica diabeticorum.

Betamethasone Sodium Phosphate and Betamethasone Acetate Injectable Suspension may also be useful in cystic tumors of an aponeurosis or tendon (ganglia).

2.4 CONTRAINDICATIONS

Betamethasone Sodium Phosphate and Betamethasone Acetate Injectable Suspension is contraindicated in patients who are hypersensitive to any components of this product (see DESCRIPTION).

Intramuscular corticosteroid preparations are contraindicated for idiopathic thrombocytopenic purpura.

2.5 WARNINGS

Betamethasone Sodium Phosphate and Betamethasone Acetate Injectable Suspension should not be administered intravenously.

2.5.1 Serious Neurologic Adverse Reactions with Epidural Administration

Serious neurologic events, some resulting in death, have been reported with epidural injection of corticosteroids. Specific events reported include, but are not limited to, spinal cord infarction, paraplegia, quadriplegia, cortical blindness, and stroke. These serious neurologic events have been reported with and without use of fluoroscopy. The safety and effectiveness of epidural administration of corticosteroids have not been established, and corticosteroids are not approved for this use.

2.5.2 General

Rare instances of anaphylactoid/anaphylactic reactions with a possibility of shock have occurred in patients receiving parenteral corticosteroid therapy (see ADVERSE REACTIONS). Use caution in patients who have a history of allergic reaction to corticosteroids.

In patients on corticosteroid therapy subjected to any unusual stress, hydrocortisone or cortisone is the drug of choice as a supplement during and after the event.

2.5.3 Cardio-Renal

Average and large doses of corticosteroids can cause elevation of blood pressure, salt and water retention, and increased excretion of potassium. These effects are less likely to occur with the synthetic derivatives except when used in large doses. Dietary salt restriction and potassium supplementation may be necessary. All corticosteroids increase calcium excretion.

Literature reports suggest an apparent association between use of corticosteroids and left ventricular free wall rupture after a recent myocardial infarction; therefore, therapy with corticosteroids should be used with great caution in these patients.

2.5.4 Endocrine

Corticosteroids can produce reversible hypothalamic pituitary adrenal (HPA) axis suppression with the potential for glucocorticosteroid insufficiency after withdrawal of treatment.

Metabolic clearance of corticosteroids is decreased in hypothyroid patients and increased in hyperthyroid patients. Changes in thyroid status of the patient may necessitate adjustment in dosage.

2.5.5 Infections

2.5.5.1 General

Patients who are on corticosteroids are more susceptible to infections than are healthy individuals. There may be decreased resistance and inability to localize infection when corticosteroids are used. Infection with any pathogen (viral, bacterial, fungal, protozoan, or helminthic) in any location of the body may be associated with the use of corticosteroids alone or in combination with other immunosuppressive agents. These infections may be mild to severe. With increasing doses of corticosteroids, the rate of occurrence of infectious complications increases. Corticosteroids may also mask some signs of current infection.

2.5.5.2 Fungal Infections

Corticosteroids may exacerbate systemic fungal infections and therefore should not be used in the presence of such infections unless they are needed to control drug reactions. There have been cases reported in which concomitant use of amphotericin B and hydrocortisone was followed by cardiac enlargement and congestive heart failure (see PRECAUTIONS, Drug Interactions, Amphotericin B Injection and Potassium-Depleting Agents section).

2.5.5.3 Special Pathogens

Latent disease may be activated or there may be an exacerbation of intercurrent infections due to pathogens, including those caused by Amoeba, Candida, Cryptococcus, Mycobacterium, Nocardia, Pneumocystis, and Toxoplasma.

It is recommended that latent amebiasis or active amebiasis be ruled out before initiating corticosteroid therapy in any patient who has spent time in the tropics or in any patient with unexplained diarrhea.

Similarly, corticosteroids should be used with great care in patients with known or suspected Strongyloides (threadworm) infestation. In such patients, corticosteroid-induced immunosuppression may lead to Strongyloides hyperinfection and dissemination with widespread larval migration, often accompanied by severe enterocolitis and potentially fatal gram-negative septicemia.

Corticosteroids should not be used in cerebral malaria.

2.5.5.4 Tuberculosis

The use of corticosteroids in active tuberculosis should be restricted to those cases of fulminating or disseminated tuberculosis in which the corticosteroid is used for the management of the disease in conjunction with an appropriate antituberculous regimen.

If corticosteroids are indicated in patients with latent tuberculosis or tuberculin reactivity, close observation is necessary as reactivation of the disease may occur. During prolonged corticosteroid therapy, these patients should receive chemoprophylaxis.

2.5.5.5 Vaccination

Administration of live or live, attenuated vaccines is contraindicated in patients receiving immunosuppressive doses of corticosteroids. Killed or inactivated vaccines may be administered. However, the response to such vaccines cannot be predicted. Immunization procedures may be undertaken in patients who are receiving corticosteroids as replacement therapy, e.g., for Addison’s disease.

2.5.5.6 Viral Infections

Chickenpox and measles can have a more serious or even fatal course in pediatric and adult patients on corticosteroids. In pediatric and adult patients who have not had these diseases, particular care should be taken to avoid exposure. The contribution of the underlying disease and/or prior corticosteroid treatment to the risk is also not known. If exposed to chickenpox, prophylaxis with varicella zoster immune globulin (VZIG) may be indicated. If exposed to measles, prophylaxis with immunoglobulin (IG) may be indicated. (See the respective package inserts for complete VZIG and IG prescribing information.) If chickenpox develops, treatment with antiviral agents should be considered.

2.5.6 Neurologic

Reports of severe medical events have been associated with the intrathecal route of administration (see ADVERSE REACTIONS, Gastrointestinal and Neurologic/Psychiatric sections).

Results from one multicenter, randomized, placebo-controlled study with methylprednisolone hemisuccinate, an intravenous corticosteroid, showed an increase in early mortality (at 2 weeks) and late mortality (at 6 months) in patients with cranial trauma who were determined not to have other clear indications for corticosteroid treatment. High doses of corticosteroids, including Betamethasone Sodium Phosphate and Betamethasone Acetate Injectable Suspension, should not be used for the treatment of traumatic brain injury.

2.5.7 Opthalmic

Use of corticosteroids may produce posterior subcapsular cataracts, increased intraocular pressure, glaucoma with possible damage to the optic nerves, and may enhance the establishment of secondary ocular infections due to bacteria, fungi, or viruses. Consider referral to an ophthalmologist for patients who develop ocular symptoms or use corticosteroid-containing products for more than 6 weeks. The use of oral corticosteroids is not recommended in the treatment of optic neuritis and may lead to an increase in the risk of new episodes. Corticosteroids should not be used in active ocular herpes simplex.

2.6 PRECAUTIONS

2.6.1 General

This product, like many other steroid formulations, is sensitive to heat. Therefore, it should not be autoclaved when it is desirable to sterilize the exterior of the vial.

The lowest possible dose of corticosteroid should be used to control the condition under treatment. When reduction in dosage is possible, the reduction should be gradual.

Since complications of treatment with glucocorticoids are dependent on the size of the dose and the duration of treatment, a risk/benefit decision must be made in each individual case as to dose and duration of treatment and as to whether daily or intermittent therapy should be used.

Kaposi’s sarcoma has been reported to occur in patients receiving corticosteroid therapy, most often for chronic conditions. Discontinuation of corticosteroids may result in clinical improvement.

2.6.2 Cardio-Renal

As sodium retention with resultant edema and potassium loss may occur in patients receiving corticosteroids, these agents should be used with caution in patients with congestive heart failure, hypertension, or renal insufficiency.

2.6.3 Endocrine

Drug-induced secondary adrenocortical insufficiency may be minimized by gradual reduction of dosage. This type of relative insufficiency may persist for months after discontinuation of therapy. Therefore, in any situation of stress occurring during that period, naturally occurring glucocorticoids (hydrocortisone cortisone), which also have salt-retaining properties, rather than betamethasone, are the appropriate choices as replacement therapy in adrenocortical deficiency states.

2.6.4 Gastrointestinal

Steroids should be used with caution in active or latent peptic ulcers, diverticulitis, fresh intestinal anastomoses, and nonspecific ulcerative colitis, since they may increase the risk of a perforation.

Signs of peritoneal irritation following gastrointestinal perforation in patients receiving corticosteroids may be minimal or absent.

There is an enhanced effect of corticosteroids in patients with cirrhosis.

2.6.5 Intra-Articular and Soft Tissue Administration

Intra-articular injected corticosteroids may be systemically absorbed.

Appropriate examination of any joint fluid present is necessary to exclude a septic process.

A marked increase in pain accompanied by local swelling, further restriction of joint motion, fever, and malaise are suggestive of septic arthritis. If this complication occurs and the diagnosis of sepsis is confirmed, appropriate antimicrobial therapy should be instituted.

Injection of a steroid into an infected site is to be avoided. Local injection of a steroid into a previously injected joint is not usually recommended.

Corticosteroid injection into unstable joints is generally not recommended.

Intra-articular injection may result in damage to joint tissues (see ADVERSE REACTIONS, Musculoskeletal section).

2.6.6 Musculoskeletal

Corticosteroids decrease bone formation and increase bone resorption both through their effect on calcium regulation (i.e., decreasing absorption and increasing excretion) and inhibition of osteoblast function. This, together with a decrease in the protein matrix of the bone secondary to an increase in protein catabolism, and reduced sex hormone production, may lead to inhibition of bone growth in pediatric patients and the development of osteoporosis at any age. Special consideration should be given to patients at increased risk of osteoporosis (i.e., postmenopausal women) before initiating corticosteroid therapy.

2.6.7 Neuro-Psychiatric

Although controlled clinical trials have shown corticosteroids to be effective in speeding the resolution of acute exacerbations of multiple sclerosis, they do not show that they affect the ultimate outcome or natural history of the disease. The studies do show that relatively high doses of corticosteroids are necessary to demonstrate a significant effect (see DOSAGE AND ADMINISTRATION).

An acute myopathy has been observed with the use of high doses of corticosteroids, most often occurring in patients with disorders with neuromuscular transmission (e.g., myasthenia gravis), or in patients receiving concomitant therapy of neuromuscular blocking drugs (e.g. pancuronium). This acute myopathy is generalized, may involve ocular and respiratory muscles, and may result in quadriparesis. Elevation of creatinine kinase may occur. Clinical improvement or recovery after stopping corticosteroids may require weeks to years.

Psychic derangements may appear when corticosteroids are used, ranging from euphoria, insomnia, mood swings, personality changes, and severe depression to frank psychotic manifestations. Also, existing emotional instability or psychotic tendencies may be aggravated by corticosteroids.

2.6.8 Information for Patients

Patients should be warned not to discontinue the use of corticosteroids abruptly or without medical supervision, to advise any medical attendants that they are taking corticosteroids and to seek medical advice at once should they develop fever or other signs of infection.

Persons who are on corticosteroids should be warned to avoid exposure to chickenpox or measles. Patients should also be advised that if they are exposed, medical advice should be sought without delay.

2.6.9 Drug Interactions

Aminoglutethimide

Aminoglutethimide may lead to a loss of corticosteroid-induced adrenal suppression.

Amphotericin B Injection and Potassium-Depleting Agents

When corticosteroids are administered concomitantly with potassium-depleting agents (i.e. amphotericin B, diuretics), patients should be observed closely for development of hypokalemia. There have been cases reported in which concomitant use of amphotericin B and hydrocortisone was followed by cardiac enlargement and congestive heart failure.

Antibiotics

Macrolide antibiotics have been reported to cause a significant decrease in corticosteroid clearance.

Anticholinesterases

Concomitant use of anticholinesterase agents and corticosteroids may produce severe weakness in patients with myasthenia gravis. If possible, anticholinesterase agents should be withdrawn at least 24 hours before initiating corticosteroid therapy.

Anticoagulants, Oral

Coadministration of corticosteroids and warfarin usually results in inhibition of response to warfarin, although there have been some conflicting reports. Therefore, coagulation indices should be monitored frequently to maintain the desired anticoagulant effect.

Antidiabetics

Because corticosteroids may increase blood glucose concentrations, dosage adjustments of antidiabetic agents may be required.

Antitubercular Drugs

Serum concentrations of isoniazid may be decreased.

Cholestyramine

Cholestyramine may increase the clearance of corticosteroids.

Cyclosporine

Increased activity of both cyclosporine and corticosteroids may occur when the two are used concurrently. Convulsions have been reported with this concurrent use.

Digitalis Glycosides

Patients on digitalis glycosides may be at increased risk of arrhythmias due to hypokalemia.

Estrogens, Including Oral Contraceptives

Estrogens may decrease the hepatic metabolism of certain corticosteroids, thereby increasing their effect.

Hepatic Enzyme Inducers (e.g., barbiturates, phenytoin, carbamazepine, rifampin)

Drugs which induce hepatic microsomal drug-metabolizing enzyme activity may enhance the metabolism of corticosteroids and require that the dosage of the corticosteroid be increased.

Interactions with Strong CYP3A4 Inhibitors

Corticosteroids (including betamethasone) are metabolized by CYP3A4.

Ketoconazole has been reported to decrease the metabolism of certain corticosteroids by up to 60%, leading to an increased risk of corticosteroid side effects.

Coadministration with other strong CYP3A4 inhibitors (e.g., itraconazole, clarithromycin, ritonavir, cobicistat-containing products) may lead to increased exposures of corticosteroids and therefore the potential for increased risk of systemic corticosteroid side effects.

Consider the benefit of coadministration versus the potential risk of systemic corticosteroid effects, in which case patients should be monitored for systemic corticosteroid side effects.

Nonsteroidal Anti-inflammatory Agents (NSAIDS)

Concomitant use of aspirin (or other nonsteroidal anti-inflammatory agents) and corticosteroids increases the risk of gastrointestinal side effects. Aspirin should be used cautiously in conjunction with corticosteroids in hypoprothrombinemia. The clearance of salicylates may be increased with concurrent use of corticosteroids.

Skin Tests

Corticosteroids may suppress reactions to skin tests.

Vaccines

Patients on prolonged corticosteroid therapy may exhibit a diminished response to toxoids and live or inactivated vaccines due to inhibition of antibody response. Corticosteroids may also potentiate the replication of some organisms contained in live attenuated vaccines. Route administration of vaccines or toxoids should be deferred until corticosteroid therapy is discontinued if possible (see WARNINGS, Infections, Vaccination section).

2.6.10 Carcinogenesis, Mutagenesis, Impairment of Fertility

No adequate studies have been conducted in animals to determine whether corticosteroids have a potential for carcinogenesis or mutagenesis.

Steroids may increase or decrease motility and number of spermatozoa in some patients.

2.6.11 Pregnancy

Teratogenic Effects

Corticosteroids have been shown to be teratogenic in many species when given in doses equivalent to the human dose. Animal studies in which corticosteroids have been given to pregnant mice, rats, and rabbits have yielded an increased incidence of cleft palate in the offspring. There are no adequate and well-controlled studies in pregnant women. Corticosteroids should be used during pregnancy only if the potential benefit justifies the potential risk to the fetus. Infants born to mothers who have received corticosteroids during pregnancy should be carefully observed for signs of hypoadrenalism.

2.6.12 Nursing Mothers

Systemically administered corticosteroids appear in human milk and could suppress growth, interfere with endogenous corticosteroid production, or cause other untoward effects. Caution should be exercised when corticosteroids are administered to a nursing woman.

2.6.13 Pediatric Use

The efficacy and safety of corticosteroids in the pediatric population are based on the well-established course of effect of corticosteroids, which is similar in pediatric and adult populations. Published studies provide evidence of efficacy and safety in pediatric patients for the treatment of nephrotic syndrome (> 2 years of age), and aggressive lymphomas and leukemias (> 1 month of age). Other indications for pediatric use of corticosteroids, e.g., severe asthma and wheezing, are based on adequate and well-controlled trials conducted in adults, on the premises that the course of the diseases and their pathophysiology are considered to be substantially similar in both populations.

The adverse effects of corticosteroids in pediatric patients are similar to those in adults (see ADVERSE REACTIONS). Like adults, pediatric patients should be carefully observed with frequent measurements of blood pressure, weight, height, intraocular pressure, and clinical evaluation for the presence of infection, psychosocial disturbances, thromboembolism, peptic ulcers, cataracts, and osteoporosis. Pediatric patients who are treated with corticosteroids by any route, including systemically administered corticosteroids, may experience a decrease in their growth velocity. This negative impact of corticosteroids on growth has been observed at low systemic doses and in the absence of laboratory evidence of HPA axis suppression (i.e., cosyntropin stimulation and basal cortisol plasma levels). Growth velocity may therefore be a more sensitive indicator of systemic corticosteroid exposure in pediatric patients than some commonly used tests of HPA axis function. The linear growth of pediatric patients treated with corticosteroids should be monitored, and the potential growth effects of prolonged treatment should be weighed against clinical benefits obtained and the availability of treatment alternatives. In order to minimize the potential growth effects of corticosteroids, pediatric patients should be titrated to the lowest effective dose.

2.6.14 Geriatric Use

No overall differences in safety or effectiveness were observed between elderly subjects and younger subjects, and other reported clinical experience has not identified differences in responses between the elderly and young patients, but greater sensitivity of some older individuals cannot be ruled out.

2.7 ADVERSE REACTIONS

(listed alphabetically, under each subsection)

Allergic Reactions

Anaphylactoid reaction, anaphylaxis, angioedema.

Cardiovascular

Bradycardia, cardiac arrest, cardiac arrhythmias, cardiac enlargement, circulatory collapse, congestive heart failure, fat embolism, hypertension, hypertrophic cardiomyopathy in premature infants, myocardial rupture following recent myocardial infarction (see WARNINGS), pulmonary edema, syncope, tachycardia, thromboembolism, thrombophlebitis, vasculitis.

Dermatologic

Acne, allergic dermatitis, cutaneous and subcutaneous atrophy, dry scaly skin, ecchymoses and petechiae, edema, erythema, hyperpigmentation, hypopigmentation, impaired wound healing, increased sweating, rash, sterile abscess, striae, suppressed reactions to skin tests, thin fragile skin, thinning scalp hair, urticaria.

Endocrine

Decreased carbohydrate and glucose tolerance, development of cushingoid state, glucosuria, hirsutism, hypertrichosis, increased requirements for insulin or oral hypoglycemic adrenocortical and pituitary unresponsiveness (particularly in times of stress, as in trauma, surgery, or illness), suppression of growth in pediatric patients.

Fluid and Electrolyte Disturbances

Congestive heart failure in susceptible patients, fluid retention, hypokalemic alkalosis, potassium loss, sodium retention.

Gastrointestinal

Abdominal distention, bowel/bladder dysfunction (after intrathecal administration), elevation in serum liver enzyme levels (usually reversible upon discontinuation), hepatomegaly, increased appetite, nausea, pancreatitis, peptic ulcer with possible perforation and hemorrhage, perforation of the small and large intestine (particularly in patients with inflammatory bowel disease), ulcerative esophagitis.

Metabolic

Negative nitrogen balance due to protein catabolism.

Musculoskeletal

Aseptic necrosis of femoral and humeral heads, calcinosis (following intra-articular or intralesional use), Charcot-like arthropathy, loss of muscle mass, muscle weakness, osteoporosis, pathologic fracture of long bones, postinjection flare (following intra-articular use), steroid myopathy, tendon rupture, vertebral compression fractures.

Neurologic/Psychiatric

Convulsions, depression, emotional instability, euphoria, headache, increased intracranial pressure with papilledema (pseudotumor cerebri) usually following discontinuation of treatment, insomnia, mood swings, neuritis, neuropathy, paresthesia, personality changes, psychic disorders, vertigo. Arachnoiditis, meningitis, paraparesis/paraplegia, and sensory disturbances have occurred after intrathecal administration (see WARNINGS, Neurologic section).

Ophthalmic

Exophthalmos, glaucoma, increased intraocular pressure, posterior subcapsular cataracts, rare instances of blindness associated with periocular injections, vision blurred.

Other

Abnormal fat deposits, decreased resistance to infection, hiccups, increased or decreased motility and number of spermatozoa, malaise, moon face, weight gain.

2.8 OVERDOSAGE

Treatment of acute overdose is by supportive and symptomatic therapy. For chronic overdosage in the face of severe disease requiring continuous steroid therapy, the dosage of the corticosteroid may be reduced only temporarily, or alternate day treatment may be introduced.

2.9 DOSAGE AND ADMINISTRATION

Benzyl alcohol as a preservative has been associated with a fatal Gasping Syndrome in premature infants and infants of low birth weight. Solutions used for further dilution of this product should be preservative-free when used in the neonate, especially the premature infant. The initial dosage of parenterally administered Betamethasone Sodium Phosphate and Betamethasone Acetate Injectable Suspension may vary from 0.25 to 9 mg per day depending on the specific disease entity being treated. However, in certain overwhelming, acute, life-threatening situations, administrations in dosages exceeding the usual dosages may be justified and may be in multiples of the oral dosages.

It Should Be Emphasized That Dosage Requirements Are Variable and Must Be Individualized on the Basis of the Disease Under Treatment and the Response of the Patient. After a favorable response is noted, the proper maintenance dosage should be determined by decreasing the initial drug dosage in small decrements at appropriate time intervals until the lowest dosage which will maintain an adequate clinical response is reached. Situations which may make dosage adjustments necessary are changes in clinical status secondary to remissions or exacerbations in the disease process, the patients individual drug responsiveness, and the effect of patient exposure to stressful situations not directly related to the disease entity under treatment. In this latter situation it may be necessary to increase the dosage of the corticosteroid for a period of time consistent with the patients condition. If after long-term therapy the drug is to be stopped, it is recommended that it be withdrawn gradually rather than abruptly.

In the treatment of acute exacerbations of multiple sclerosis, daily doses of 30 mg of betamethasone for a week followed by 12 mg every other day for 1 month are recommended (see PRECAUTIONS, Neuro-psychiatric section).

In pediatric patients, the initial dose of betamethasone may vary depending on the specific disease entity being treated. The range of initial doses is 0.02 to 0.3 mg/kg/day in three or four divided doses (0.6 to 9 mg/m^2bsa/day).

For the purpose of comparison, the following is the equivalent milligram dosage of the various glucocorticoids:
Cortisone, 25 | Triamcinolone, 4
Hydrocortisone, 20 | Paramethasone, 2
Prednisolone, 5 | Betamethasone, 0.75
Prednisone, 5 | Dexamethasone, 0.75
Methylprednisolone, 4

These dose relationships apply only to oral or intravenous administration of these compounds. When these substances or their derivatives are injected intramuscularly or into joint spaces, their relative properties may be greatly altered.

If coadministration of a local anesthetic is desired, Betamethasone Sodium Phosphate and Betamethasone Acetate Injectable Suspension may be mixed with 1% or 2% lidocaine hydrochloride, using the formulations which do not contain parabens. Similar local anesthetics may also be used. Diluents containing methylparaben, propylparaben, phenol, etc., should be avoided, since these compounds may cause flocculation of the steroid. The required dose of Betamethasone Sodium Phosphate and Betamethasone Acetate Injectable Suspension is first withdrawn from the vial into the syringe. The local anesthetic is then drawn in, and the syringe shaken briefly. Do not inject local anesthetics into the vial of Betamethasone Sodium Phosphate and Betamethasone Acetate Injectable Suspension.

2.9.1 Bursitis, Tenosynovitis, Peritendinitis

In acute subdeltoid, subacromial, olecranon, and prepatellar bursitis, one intrabursal injection of 1 mL Betamethasone Sodium Phosphate and Betamethasone Acetate Injectable Suspension can relieve pain and restore full range of movement. Several intrabursal injections of corticosteroids are usually required in recurrent acute bursitis and in acute exacerbations of chronic bursitis. Partial relief of pain and some increase in mobility can be expected in both conditions after one or two injections. Chronic bursitis may be treated with reduced dosage once the acute condition is controlled. In tenosynovitis and tendinitis, three or four local injections at intervals of 1 to 2 weeks between injections are given in most cases. Injections should be made into the affected tendon sheaths rather than into the tendons themselves. In ganglions of joint capsules and tendon sheaths, injection of 0.5 mL directly into the ganglion cysts has produced marked reduction in the size of the lesions.

2.9.2 Rheumatoid Arthritis and Osteoarthritis

Following intra-articular administration of 0.5 to 2 mL of Betamethasone Sodium Phosphate and Betamethasone Acetate Injectable Suspension, relief of pain, soreness, and stiffness may be experienced. Duration of relief varies widely in both diseases. Intra-articular Injection of Betamethasone Sodium Phosphate and Betamethasone Acetate Injectable Suspension is well tolerated in joints and periarticular tissues. There is virtually no pain on injection, and the secondary flare that sometimes occurs a few hours after intra-articular injection of corticosteroids has not been reported with Betamethasone Sodium Phosphate and Betamethasone Acetate Injectable Suspension. Using sterile technique, a 20- to 24-gauge needle on an empty syringe is inserted into the synovial cavity and a few drops of synovial fluid are withdrawn to confirm that the needle is in the joint. The aspirating syringe is replaced by a syringe containing Betamethasone Sodium Phosphate and Betamethasone Acetate Injectable Suspension and injection is then made into the joint.

Recommended Doses for Intra-articular Injection
Size of Joint | Location | Dose (mL)
Very Large | Hip | 1-2
Large | Knee, ankle, shoulder | 1
Medium | Elbow, wrist | 0.5-1
Small (metacarpophalangeal, interphalangeal) (sternoclavicular) | Hand, chest | 0.25 to 0.5

A portion of the administered dose of Betamethasone Sodium Phosphate and Betamethasone Acetate Injectable Suspension is absorbed systemically following intra-articular injection. In patients being treated concomitantly with oral or parenteral corticosteroids, especially those receiving large doses, the systemic absorption of the drug should be considered in determining intra-articular dosage.

2.9.3 Dermatologic Conditions

In intralesional treatment, 0.2 mL/cm^2 of Betamethasone Sodium Phosphate and Betamethasone Acetate Injectable Suspension is injected intradermally (not subcutaneously) using a tuberculin syringe with a 25-gauge, 1/2-inch needle. Care should be taken to deposit a uniform depot of medication intradermally. A total of no more than 1 mL at weekly intervals is recommended.

2.9.4 Disorders of the Foot

A tuberculin syringe with a 25-gauge, 3/4-inch needle is suitable for most injections into the foot. The following doses are recommended at intervals of 3 days to a week.

Diagnosis | Betamethasone Sodium Phosphate and Betamethasone Acetate Injectable Suspension Dose (mL)
Bursitis under heloma durum or heloma molle | 0.25 to 0.5
under calcaneal spur | 0.5
over hallux rigidus of digiti quinti varus | 0.5
Tenosynovitis, periostitis of cuboid | 0.5
Acute gouty arthritis | 0.5 to 1

2.10 HOW SUPPLIED

NDC 0517-0720-01:

Betamethasone Sodium Phosphate and Betamethasone Acetate Injectable Suspension, 5 mL multiple dose vial; box of one. Inactive ingredients per mL: 7.1 mg dibasic sodium phosphate anhydrous; 3.4 mg monobasic sodium phosphate monohydrate; 0.1 mg edetate disodium; and 0.2 mg benzalkonium chloride as preservative.

SHAKE WELL BEFORE USING.

Store at 20° to 25°C (68° to 77°F); excursions permitted to 15° to 30°C (59° to 86°F) [See USP Controlled Room Temperature].

Protect from light.

Rx only

Revised July 2018

MCKESSON ALCOHOL PREP PAD- isopropyl alcohol swab

Drug Facts

Active ingredient

Isopropyl Alcohol 70% v/v

Purpose

First Aid Antiseptic

Use

For preparation of the skin prior to an injection

Warnings

- For external use only
- Flammable, keep away from fire or flame
- Do not use with electrocautery procedures
- Do not use in the eyes
- Do not apply to irritated skin
- Stop use if pain, irritation, redness, or swelling occurs, discontinue use and consult a physician.

KEEP OUT OF REACH OF CHILDREN

- Keep out from reach of children. If swallowed, get medical help or contact a Poison Control Center right away.

Directions

- Open packet
- Remove pad
- Apply topically as needed to cleanse intended area. Discard after single use.

Other information

- Store at room temperature 59-86°F (15-30°C)
- Contents sterile in unopened, undamaged package

Inactive ingredients

purified water

H-Paxin Injection System

Contents:

1 - 50mL 2% Lidocaine HCl (20mg/mL)

1 - 50mL .25 Bupivacaine HCl (2.5mg/mL)

1 - 5mL Betamethasone Sodium Phosphate and Betamethasone Acetate (6mg/mL)

1 - 3cc Syringe w/ 18-22 Gauge 1-1 1/2 in Needle (Draw)

1 - 22-27 Gauge 1-1 1/2 inch Needle (Administer)

1 - 3x3 Gauze Sponge Sterile Square

1 - Bandage 1x3 in

4 - Alcohol Prep Pads

Assembled and Distributed by IT3 Medical, LLC 190 E Stacy Road; STE 306-298 Allen, TX 75002-8734

For questions or comments: info@IT3-Medical.com, www.IT3-Medical.com